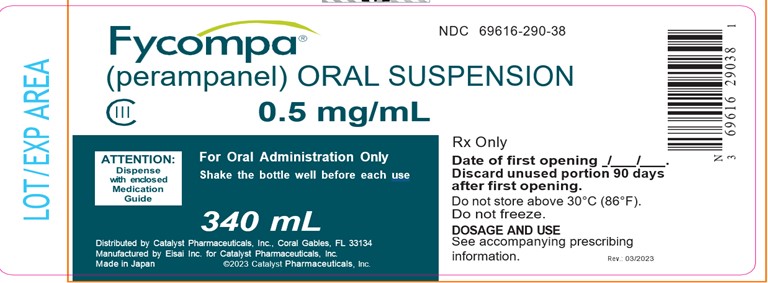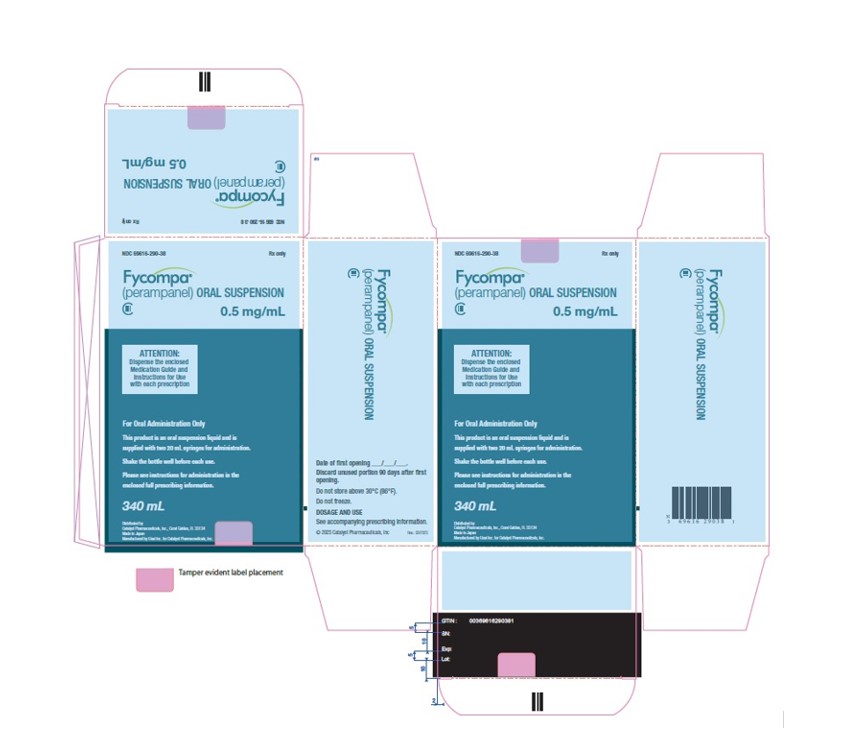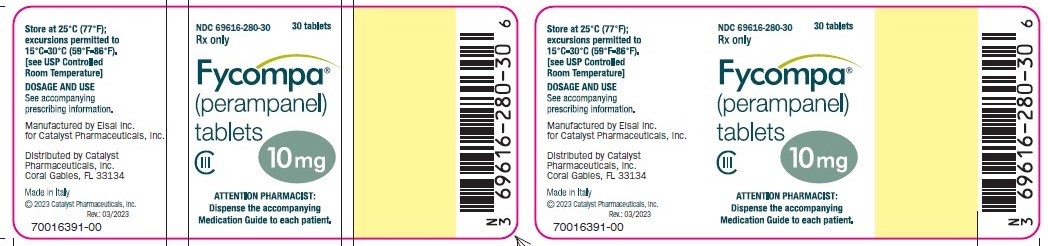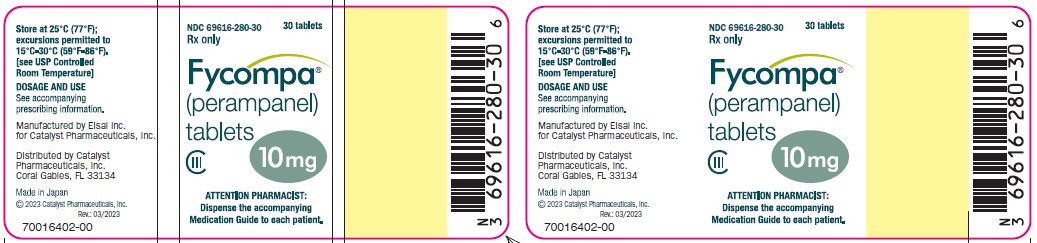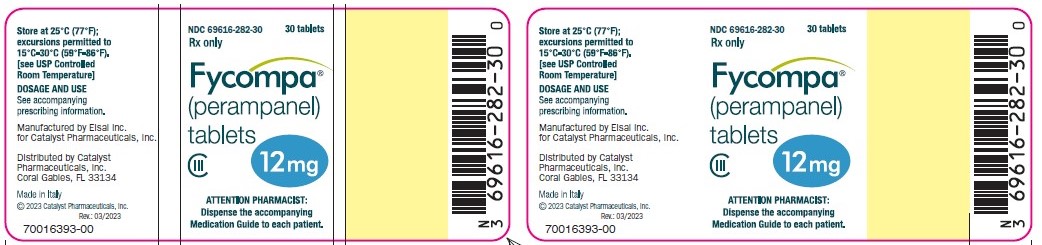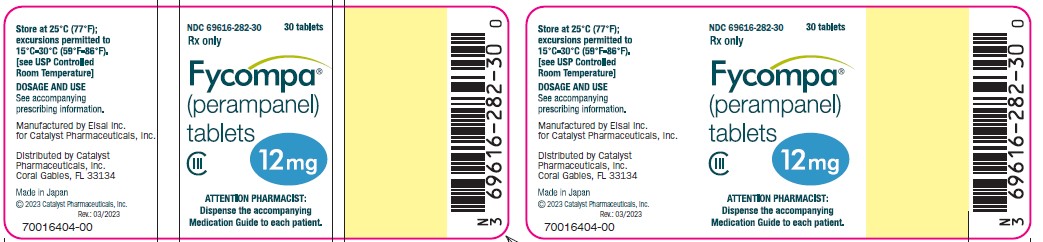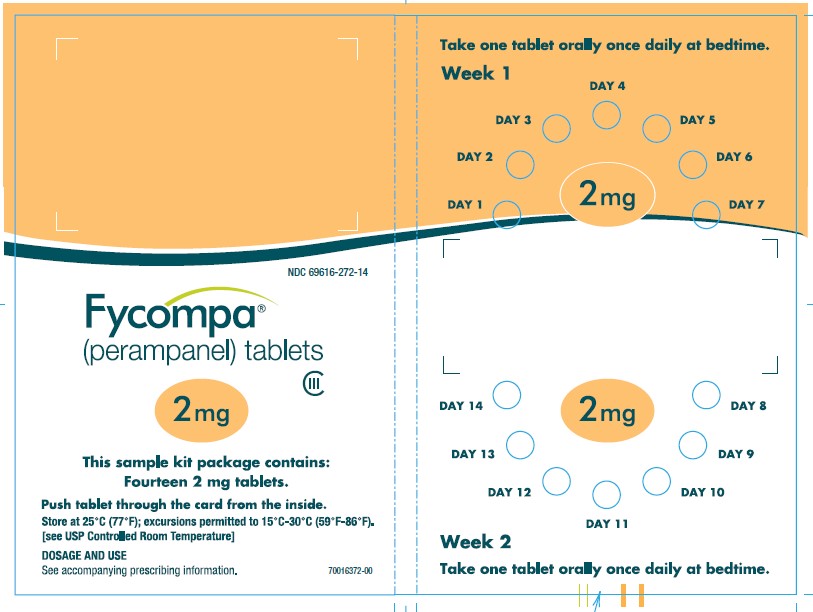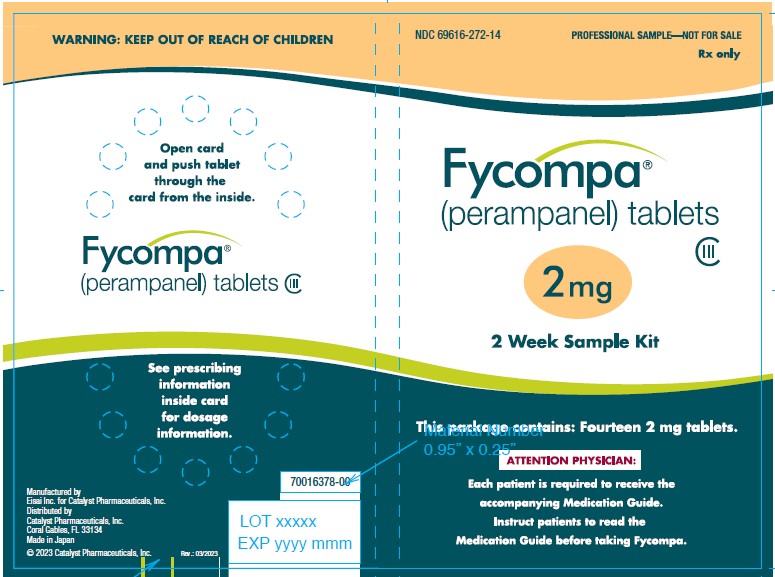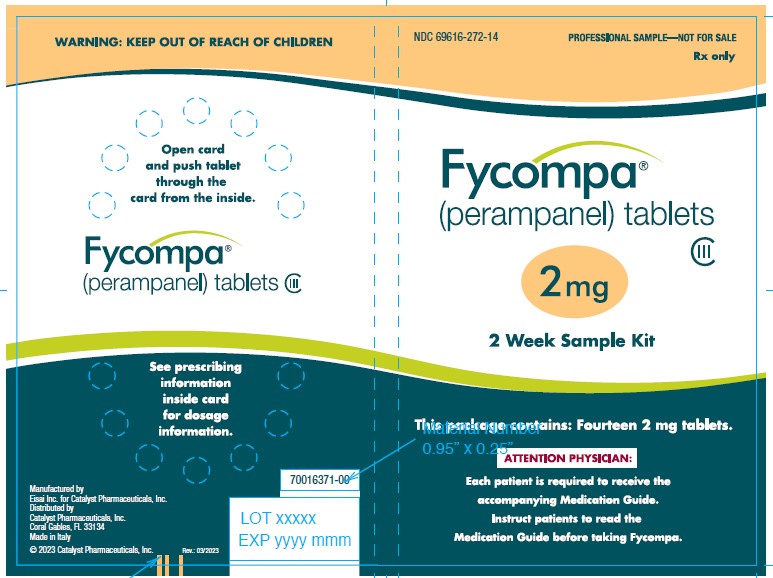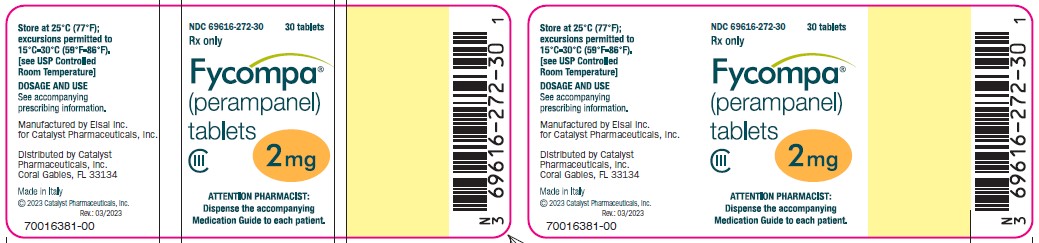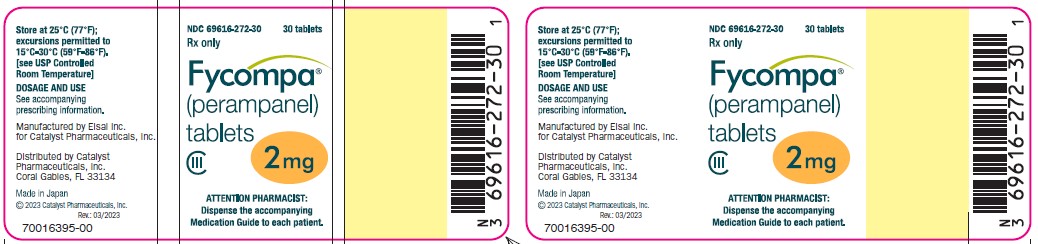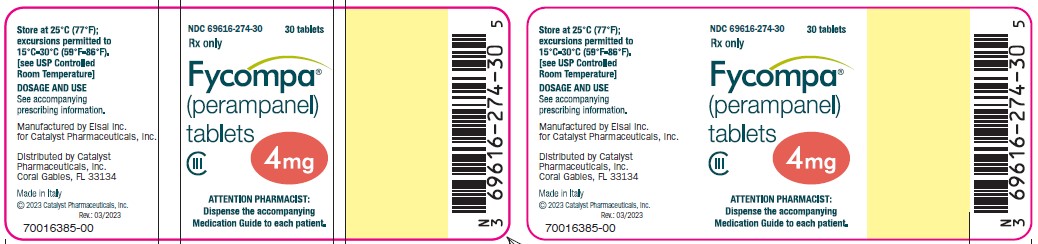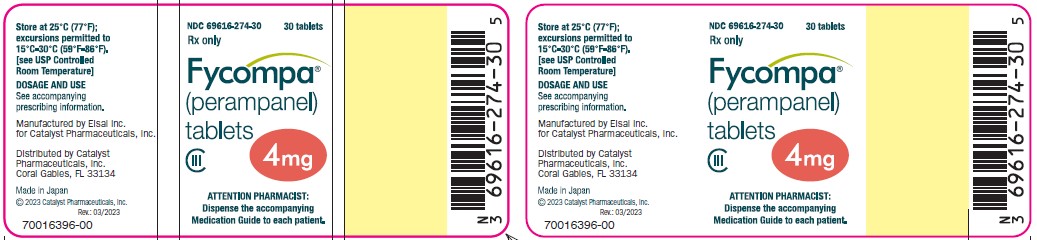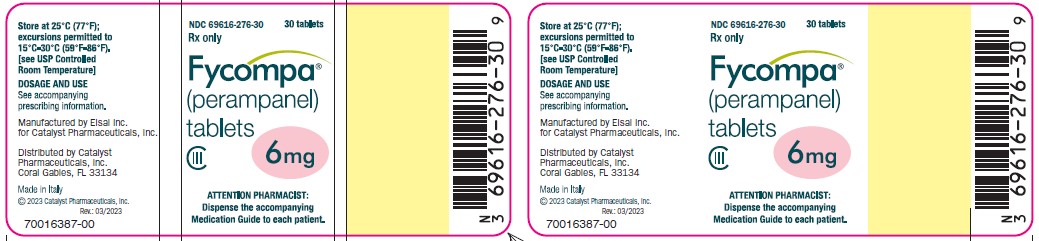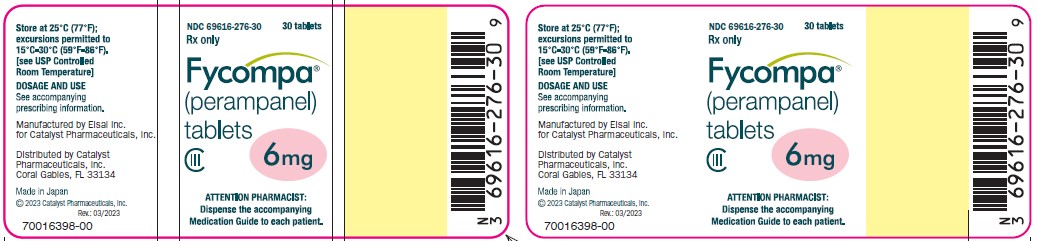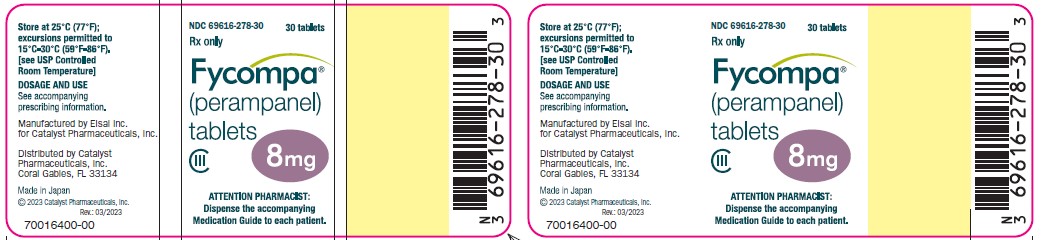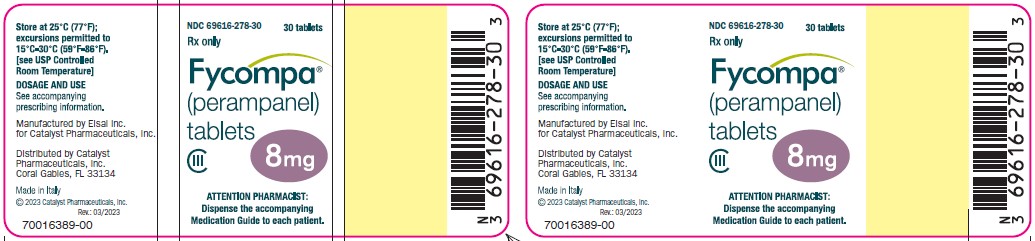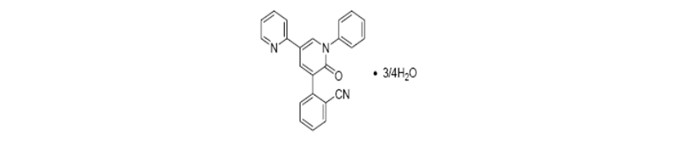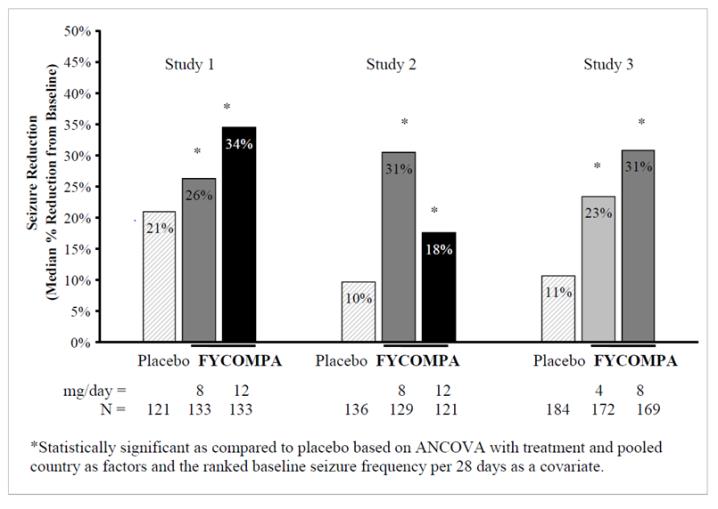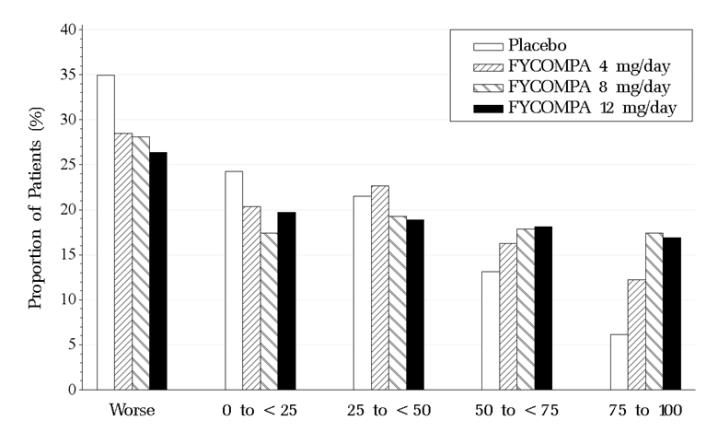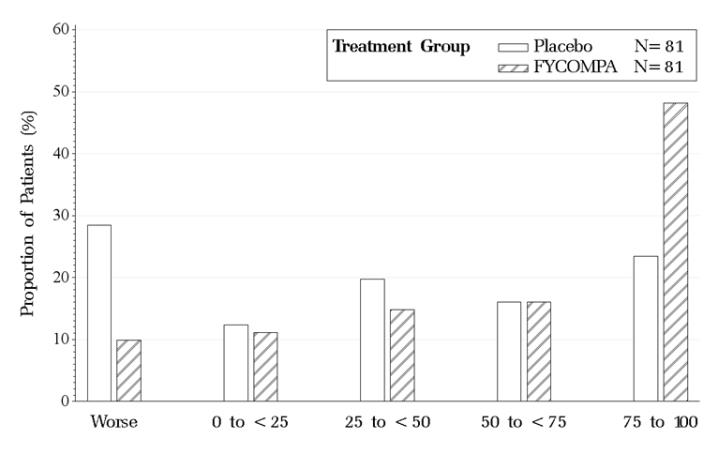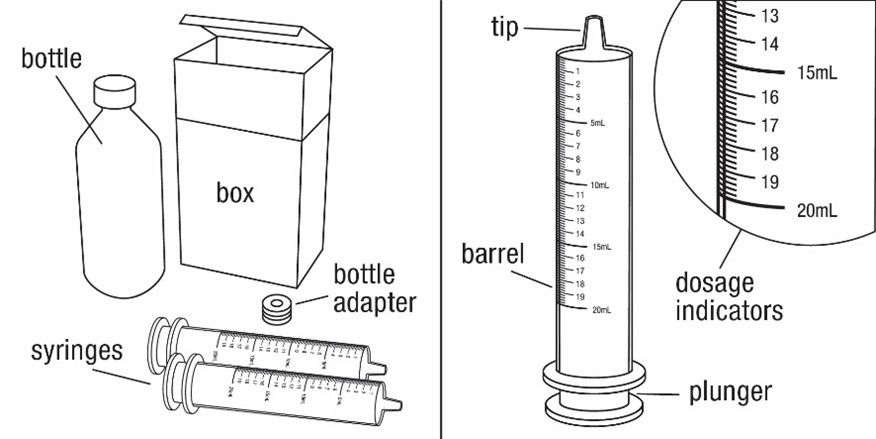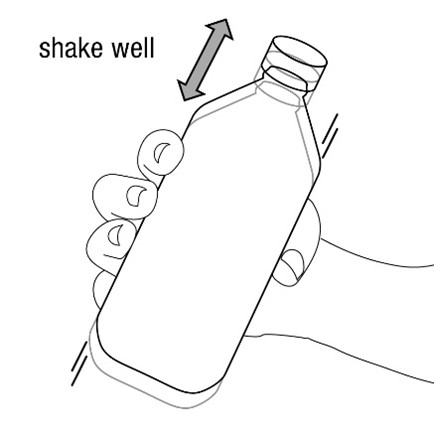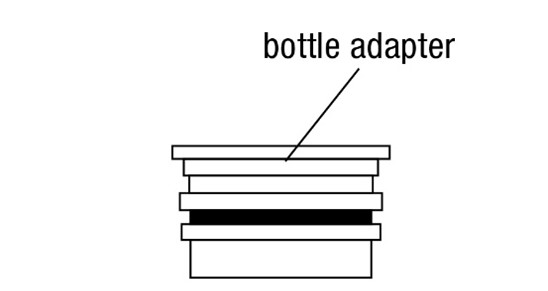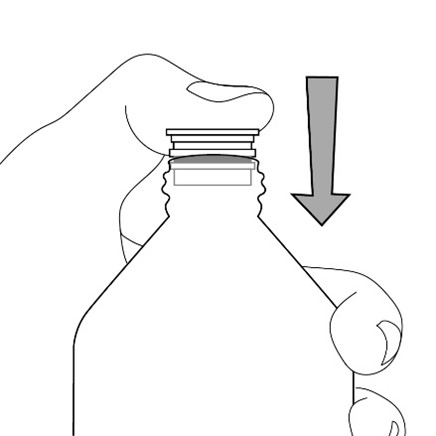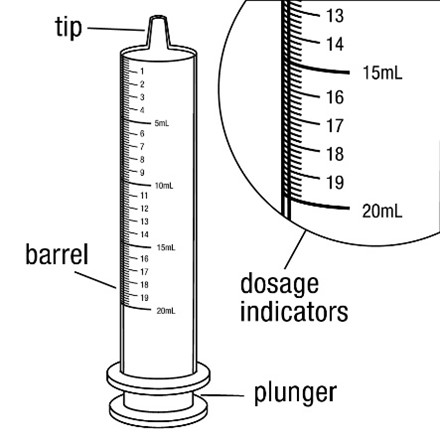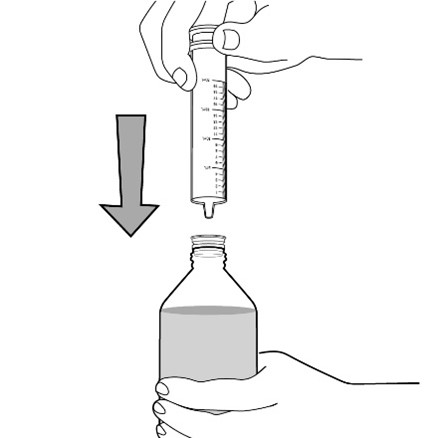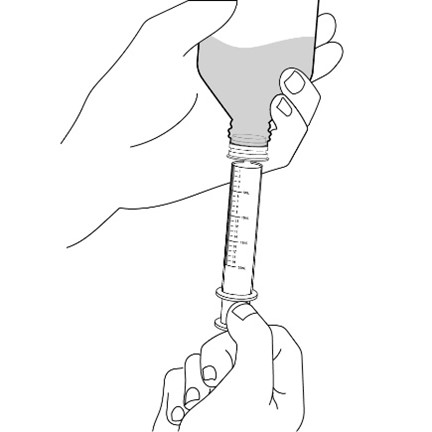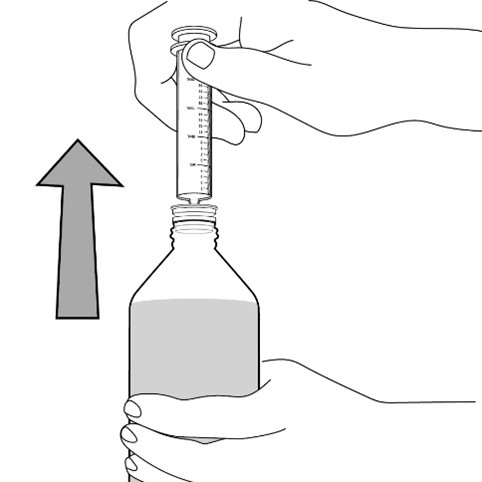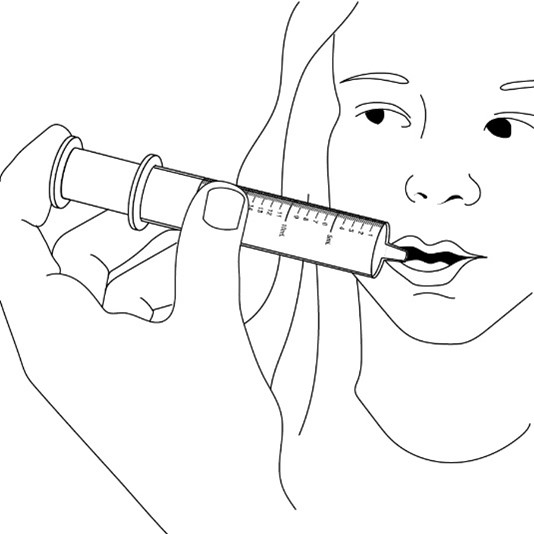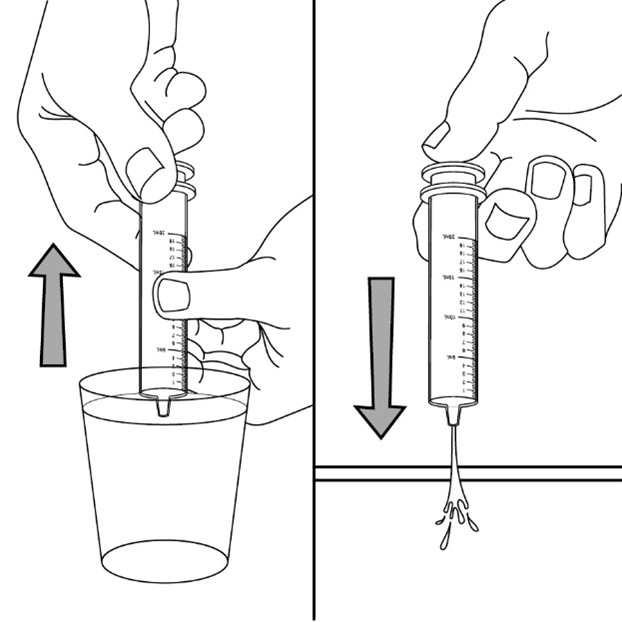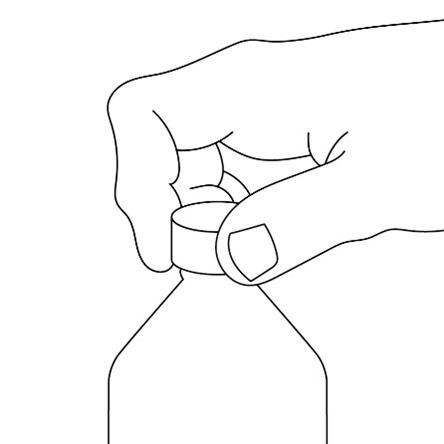 DRUG LABEL: Fycompa
NDC: 69616-272 | Form: TABLET
Manufacturer: Catalyst Pharmaceuticals, Inc.
Category: prescription | Type: HUMAN PRESCRIPTION DRUG LABEL
Date: 20240105
DEA Schedule: CIII

ACTIVE INGREDIENTS: PERAMPANEL 2 mg/1 1
INACTIVE INGREDIENTS: LACTOSE MONOHYDRATE; LOW-SUBSTITUTED HYDROXYPROPYL CELLULOSE (11% HYDROXYPROPYL; 120000 MW); POVIDONE; MAGNESIUM STEARATE; HYPROMELLOSES; POLYETHYLENE GLYCOL 8000; TALC; TITANIUM DIOXIDE; FERRIC OXIDE YELLOW; FERRIC OXIDE RED

HIGHLIGHTS OF PRESCRIBING INFORMATION

These highlights do not include all the information needed to use FYCOMPA®
safely and effectively. See full prescribing information for FYCOMPA®.
FYCOMPA®(perampanel) tablets, for oral use, CIII
FYCOMPA® (perampanel) oral suspension, CIII
Initial U.S. Approval: 2012

WARNING: SERIOUS PSYCHIATRIC AND BEHAVIORAL REACTIONS

See full prescribing information for complete boxed warning.

- Serious or life-threatening psychiatric and behavioral adverse reactions including aggression, hostility, irritability, anger, and homicidal ideation and threats have been reported in patients taking FYCOMPA (5.1)
- Monitor patients for these reactions as well as for changes in mood, behavior, or personality that are not typical for the patient, particularly during the titration period and at higher doses (5.1)
- FYCOMPA should be reduced if these symptoms occur and should be discontinued immediately if symptoms are severe or are worsening (5.1)

1 INDICATIONS AND USAGE

FYCOMPA, a non-competitive AMPA glutamate receptor antagonist, is indicated for:

- Treatment of partial-onset seizures with or without secondarily generalized seizures in patients with epilepsy 4 years of age and older (1.1)
- Adjunctive therapy in the treatment of primary generalized tonic-clonic seizures in patients with epilepsy 12 years of age and older (1.2)

2 DOSAGE AND ADMINISTRATION

Dosing in the absence of moderate or strong CYP3A4 inducers

- Starting dose: 2 mg once daily orally at bedtime (2.1, 2.2)
- May increase dose based on clinical response and tolerability by increments of 2 mg once daily no more frequently than at weekly intervals (2.1, 2.2)
- Recommended maintenance dose in monotherapy or adjunctive therapy for partial-onset seizures: 8 mg to 12 mg once daily at bedtime (2.1)
- Recommended maintenance dose in adjunctive therapy for primary generalized tonic-clonic seizures: 8 mg once daily at bedtime (2.2)
- Measure oral suspension using provided adaptor and dosing syringe (2.7)

Dosing in the presence of concomitant moderate or strong CYP3A4 inducers: see section 2.3

Specific Populations

- Mild and Moderate Hepatic Impairment: Maximum recommended daily dose is 6 mg (mild) and 4 mg (moderate) once daily at bedtime (2.4)
- Severe Hepatic Impairment: Not recommended (2.4)
- Severe Renal Impairment or on Hemodialysis: Not recommended (2.5)
- Elderly: Increase dose no more frequently than every 2 weeks (2.6)

3 DOSAGE FORMS AND STRENGTHS

- Tablets: 2 mg, 4 mg, 6 mg, 8 mg, 10 mg, and 12 mg (3)
- Oral Suspension: 0.5 mg/mL (3)

4 CONTRAINDICATIONS

None (4)

5 WARNINGS AND PRECAUTIONS

- Suicidal Behavior and Ideation: Monitor for suicidal thoughts or behavior (5.2)
- Neurologic Effects: Monitor for dizziness, gait disturbance, somnolence, and fatigue (5.3)
- Patients should use caution when driving or operating machinery (5.3)
- Falls: Monitor for falls and injuries (5.4)
- Drug Reaction with Eosinophilia and Systemic Symptoms (DRESS)/ Multi-Organ Hypersensitivity: Discontinue if no alternate etiology (5.5)
- Withdrawal of Antiepileptic Drugs: In patients with epilepsy, there may be an increase in seizure frequency (5.6)

6 ADVERSE REACTIONS

Most common adverse reactions (≥5% and ≥1% higher than placebo) include dizziness, somnolence, fatigue, irritability, falls, nausea, weight gain, vertigo, ataxia, headache, vomiting, contusion, abdominal pain, and anxiety (6.1)

To report SUSPECTED ADVERSE REACTIONS, contact Catalyst Pharmaceuticals at 1-844-347-3277 or FDA at 1-800-FDA-1088 or www.fda.gov/medwatch

7 DRUG INTERACTIONS

- Contraceptives: 12 mg once daily may decrease the effectiveness of hormonal contraceptives containing levonorgestrel (7.1)
- Moderate and Strong CYP3A4 Inducers (including carbamazepine, oxcarbazepine, and phenytoin): increase clearance of perampanel and decrease perampanel plasma concentrations. When moderate or strong CYP3A4 inducers are introduced or withdrawn, monitor patients closely. Dose adjustment of FYCOMPA may be necessary (2.3, 7.2)

8 USE IN SPECIFIC POPULATIONS

Pregnancy: Based on animal data, may cause fetal harm (8.1)

FULL PRESCRIBING INFORMATION

WARNING: SERIOUS PSYCHIATRIC AND BEHAVIORAL REACTIONS

- Serious or life-threatening psychiatric and behavioral adverse reactions including aggression, hostility, irritability, anger, and homicidal ideation and threats have been reported in patients taking FYCOMPA (5.1).
- These reactions occurred in patients with and without prior psychiatric history, prior aggressive behavior, or concomitant use of medications associated with hostility and aggression (5.1).
- Advise patients and caregivers to contact a healthcare provider immediately if any of these reactions or changes in mood, behavior, or personality that are not typical for the patient are observed while taking FYCOMPA or after discontinuing FYCOMPA (5.1).
- Closely monitor patients particularly during the titration period and at higher doses (5.1).
- FYCOMPA should be reduced if these symptoms occur and should be discontinued immediately if symptoms are severe or are worsening (5.1).

1 INDICATIONS AND USAGE

1.1 Partial-Onset Seizures

FYCOMPA is indicated for the treatment of partial-onset seizures with or without secondarily generalized seizures in patients with epilepsy 4 years of age and older.

1.2 Primary Generalized Tonic-Clonic Seizures

FYCOMPA is indicated as adjunctive therapy for the treatment of primary generalized tonic-clonic seizures in patients with epilepsy 12 years of age and older.

2 DOSAGE AND ADMINISTRATION

2.1 Dosage for Partial-Onset Seizures

Monotherapy or Adjunctive Therapy

The recommended starting dosage of FYCOMPA in adults and pediatric patients 4 years of age and older is 2 mg once daily taken orally at bedtime. Increase dosage no more frequently than at weekly intervals by increments of 2 mg once daily based on individual clinical response and tolerability.

The recommended maintenance dose range is 8 mg to 12 mg once daily, although some patients may respond to a dose of 4 mg daily. A dose of 12 mg once daily resulted in somewhat greater reductions in seizure rates than the dose of 8 mg once daily, but with a substantial increase in adverse reactions.

Dosage adjustment is recommended with concomitant use of moderate or strong CYP3A4 enzyme inducing drugs, which include certain antiepileptic drugs (AEDs) [see Dosage and Administration (2.3)].

2.2 Dosage for Primary Generalized Tonic-Clonic Seizures

Adjunctive Therapy

The recommended starting dosage of FYCOMPA in adults and pediatric patients 12 years of age and older is 2 mg once daily taken orally at bedtime. Increase dosage no more frequently than at weekly intervals by increments of 2 mg once daily based on individual clinical response and tolerability.

The recommended maintenance dose is 8 mg once daily taken at bedtime. Patients who are tolerating FYCOMPA at 8 mg once daily and require further reduction of seizures may benefit from a dose increase up to 12 mg once daily if tolerated.

Dosage adjustment is recommended with concomitant use of moderate or strong CYP3A4 enzyme inducing drugs, which include certain AEDs [see Dosage and Administration (2.3)].

2.3 Dosage Modifications with Concomitant Use of Moderate or Strong CYP3A4 Enzyme Inducers

Moderate and strong CYP3A4 inducers, including enzyme-inducing AEDs such as phenytoin, carbamazepine, and oxcarbazepine, cause a reduction in FYCOMPA plasma levels [see Drug Interactions (7.2), Clinical Pharmacology (12.3)]. Therefore, in adults and pediatric patients 4 years of age and older receiving these concomitant enzyme-inducing drugs, the recommended starting dosage of FYCOMPA is 4 mg once daily taken orally at bedtime.

Increase dosage by increments of 2 mg once daily based on individual clinical response and tolerability, no more frequently than at weekly intervals. A maintenance dose has not been established in clinical trials. The highest dose studied in patients on concomitant enzyme-inducing AEDs was 12 mg once daily.

When moderate or strong CYP3A4 inducers are introduced or withdrawn from a patient’s treatment regimen, the patient should be closely monitored for clinical response and tolerability. Dose adjustment of FYCOMPA may be necessary.

2.4 Dosage Adjustment in Patients with Hepatic Impairment

In patients with mild and moderate hepatic impairment, the starting dose of FYCOMPA is 2 mg once daily. Increase dosage by increments of 2 mg once daily no more frequently than every 2 weeks. The maximum recommended daily dose is 6 mg for patients with mild hepatic impairment and 4 mg for patients with moderate hepatic impairment. FYCOMPA is not recommended for use in patients with severe hepatic impairment [see Use in Specific Populations (8.6), Clinical Pharmacology (12.3)].

2.5 Dosage Information for Patients with Renal Impairment

FYCOMPA can be used in patients with moderate renal impairment with close monitoring. A slower titration may be considered, based on clinical response and tolerability. FYCOMPA is not recommended in patients with severe renal impairment or patients undergoing hemodialysis [see Use in Specific Populations (8.7), Clinical Pharmacology (12.3)].

2.6 Dosage Information for Elderly Patients

In elderly patients, increase dosage no more frequently than every 2 weeks during titration [see Use in Specific Populations (8.5)].

2.7 Administration of Oral Suspension

FYCOMPA oral suspension, 0.5 mg/mL, should be shaken well before every administration. The provided adapter and graduated oral dosing syringe should be used to administer the oral suspension. A household teaspoon or tablespoon is not an adequate measuring device. The adapter, which is supplied in the product carton, should be inserted firmly into the neck of the bottle before use and remain in place for the duration of the usage of the bottle. The dosing syringe should be inserted into the adapter and the dose withdrawn from the inverted bottle. The cap should be replaced after each use. The cap fits properly when the adapter is in place [see Instructions for Use].

Discard any unused FYCOMPA oral suspension remaining 90 days after first opening the bottle.

3 DOSAGE FORMS AND STRENGTHS

Tablets

- 2 mg tablets: orange, round, debossed with “2” on one side and “Є 275” on the other.
- 4 mg tablets: red, round, debossed with “4” on one side and “Є 277” on the other.
- 6 mg tablets: pink, round, debossed with “6” on one side and “Є 294” on the other.
- 8 mg tablets: purple, round, debossed with “8” on one side and “Є 295” on the other.
- 10 mg tablets: green, round, debossed with “10” on one side and “Є 296” on the other.
- 12 mg tablets: blue, round, debossed with “12” on one side and “Є 297” on the other.

Oral Suspension

0.5 mg/mL white to off-white opaque liquid suspension for oral administration.

4 CONTRAINDICATIONS

None.

5 WARNINGS AND PRECAUTIONS

5.1 Serious Psychiatric and Behavioral Reactions

In the controlled partial-onset seizure clinical trials, hostility- and aggression-related adverse reactions occurred in 12% and 20% of patients randomized to receive FYCOMPA at doses of 8 mg and 12 mg per day, respectively, compared to 6% of patients in the placebo group. These effects were dose-related and generally appeared within the first 6 weeks of treatment, although new events continued to be observed through more than 37 weeks. FYCOMPA-treated patients experienced more hostility- and aggression-related adverse reactions that were serious, severe, and led to dose reduction, interruption, and discontinuation more frequently than placebo-treated patients.

In general, in placebo-controlled partial-onset seizure clinical trials, neuropsychiatric events were reported more frequently in patients being treated with FYCOMPA than in patients taking placebo. These events included irritability, aggression, anger, and anxiety, which occurred in 2% or greater of FYCOMPA-treated patients and twice as frequently as in placebo-treated patients. Other symptoms that occurred with FYCOMPA and were more common than with placebo included belligerence, affect lability, agitation, and physical assault. Some of these events were reported as serious and life-threatening. Homicidal ideation and/or threat were exhibited in 0.1% of 4,368 FYCOMPA-treated patients in controlled and open label trials, including non-epilepsy trials. Homicidal ideation and/or threat have also been reported postmarketing in patients treated with FYCOMPA.

In the partial-onset seizure clinical trials, these events occurred in patients with and without prior psychiatric history, prior aggressive behavior, or concomitant use of medications associated with hostility and aggression. Some patients experienced worsening of their pre-existing psychiatric conditions. Patients with active psychotic disorders and unstable recurrent affective disorders were excluded from the clinical trials. The combination of alcohol and FYCOMPA significantly worsened mood and increased anger. Patients taking FYCOMPA should avoid the use of alcohol [see Drug Interactions (7.3)].

Similar serious psychiatric and behavioral events were observed in the primary generalized tonic-clonic seizure clinical trial.

In healthy volunteers taking FYCOMPA, observed psychiatric events included paranoia, euphoric mood, agitation, anger, mental status changes, and disorientation/confusional state.

In the non-epilepsy trials, psychiatric events that occurred in perampanel-treated patients more often than placebo-treated patients included disorientation, delusion, and paranoia.

In the postmarketing setting, there have been reports of psychosis (acute psychosis, hallucinations, delusions, paranoia) and delirium (delirium, confusional state, disorientation, memory impairment) in patients treated with FYCOMPA [see Adverse Reactions (6.2)].

Patients, their caregivers, and families should be informed that FYCOMPA may increase the risk of psychiatric events. Patients should be monitored during treatment and for at least 1 month after the last dose of FYCOMPA, and especially when taking higher doses and during the initial few weeks of drug therapy (titration period) or at other times of dose increases. Dose of FYCOMPA should be reduced if these symptoms occur. Permanently discontinue FYCOMPA for persistent severe or worsening psychiatric symptoms or behaviors and refer for psychiatric evaluation.

5.2 Suicidal Behavior and Ideation

Antiepileptic drugs (AEDs), including FYCOMPA, increase the risk of suicidal thoughts or behavior in patients taking these drugs for any indication. Patients treated with any AED for any indication should be monitored for the emergence or worsening of depression, suicidal thoughts or behavior, and/or any unusual changes in mood or behavior.

Pooled analyses of 199 placebo-controlled clinical trials (mono- and adjunctive therapy) of 11 different AEDs showed that patients randomized to one of the AEDs had approximately twice the risk (adjusted Relative Risk 1.8, 95% CI: 1.2, 2.7) of suicidal thinking or behavior compared to patients randomized to placebo. In these trials, which had a median treatment duration of 12 weeks, the estimated incidence of suicidal behavior or ideation among 27,863 AED-treated patients was 0.43%, compared to 0.24% among 16,029 placebo-treated patients, representing an increase of approximately one case of suicidal thinking or behavior for every 530 patients treated. There were four suicides in drug-treated patients in the trials and none in placebo-treated patients, but the number is too small to allow any conclusion about drug effect on suicide.

The increased risk of suicidal thoughts or behavior with AEDs was observed as early as 1 week after starting drug treatment with AEDs and persisted for the duration of treatment assessed. Because most trials included in the analysis did not extend beyond 24 weeks, the risk of suicidal thoughts or behavior beyond 24 weeks could not be assessed.

The risk of suicidal thoughts or behavior was generally consistent among drugs in the data analyzed. The finding of increased risk with AEDs of varying mechanisms of action and across a range of indications suggests that the risk applies to all AEDs used for any indication. The risk did not vary substantially by age (5-100 years) in the clinical trials analyzed.

Table 1 shows absolute and relative risk by indication for all evaluated AEDs.

Table 1. Risk by indication for antiepileptic drugs in the pooled analysis
Indication | Placebo Patients; with Events per; 1000 Patients | Drug Patients with; Events per 1000; patients | Relative Risk:; Incidence of Events; in drug Patients/; Incidence in Placebo; Patients | Risk Difference:; Additional Drug; Patients with Events; per 1000 Patients
Epilepsy | 1.0 | 3.4 | 3.5 | 2.4
Psychiatric | 5.7 | 8.5 | 1.5 | 2.9
Other | 1.0 | 1.8 | 1.9 | 0.9
Total | 2.4 | 4.3 | 1.8 | 1.9

The relative risk for suicidal thoughts or behavior was higher in clinical trials for epilepsy than in clinical trials for psychiatric or other conditions, but the absolute risk differences were similar for the epilepsy and psychiatric indications.

Anyone considering prescribing FYCOMPA or any other AED must balance the risk of suicidal thoughts or behavior with the risk of untreated illness. Epilepsy and many other illnesses for which AEDs are prescribed are themselves associated with morbidity and mortality and an increased risk of suicidal thoughts and behavior. Should suicidal thoughts and behavior emerge during treatment, the prescriber needs to consider whether the emergence of these symptoms in any given patient may be related to the illness being treated.

5.3 Neurologic Effects

Dizziness and Gait Disturbance

FYCOMPA caused dose-related increases in events related to dizziness and disturbance in gait or coordination [see Adverse Reactions (6.1)]. In the controlled partial-onset seizure clinical trials, dizziness and vertigo were reported in 35% and 47% of patients randomized to receive FYCOMPA at doses of 8 mg and 12 mg per day, respectively, compared to 10% of placebo-treated patients. The gait disturbance related events (including ataxia, gait disturbance, balance disorder, and abnormal coordination) were reported in 12% and 16% of patients randomized to receive FYCOMPA at doses of 8 mg and 12 mg per day, respectively, compared to 2% of placebo-treated patients. Elderly patients had an increased risk of these adverse reactions compared to younger adults and pediatric patients.

These adverse reactions occurred mostly during the titration phase and led to discontinuation in 3% of FYCOMPA-treated patients compared to 1% of placebo-treated patients.

These adverse reactions were also observed in the primary generalized tonic-clonic seizure clinical trial.

Somnolence and Fatigue

FYCOMPA caused dose-dependent increases in somnolence and fatigue-related events (including fatigue, asthenia, and lethargy).

In the controlled partial-onset seizure clinical trials, 16% and 18% of patients randomized to receive FYCOMPA at doses of 8 mg and 12 mg per day, respectively, reported somnolence compared to 7% of placebo patients. In the controlled partial-onset seizure clinical trials, 12% and 15% of patients randomized to receive FYCOMPA at doses of 8 mg and 12 mg per day, respectively, reported fatigue-related events compared to 5% of placebo patients. Somnolence or fatigue-related events led to discontinuation in 2% of FYCOMPA-treated patients and 0.5% of placebo-treated patients. Elderly patients had an increased risk of these adverse reactions compared to younger adults and pediatric patients.

In the controlled partial-onset seizure clinical trials, these adverse reactions occurred mostly during the titration phase.

These adverse reactions were also observed in the primary generalized tonic-clonic seizure clinical trial.

Risk Amelioration

Prescribers should advise patients against engaging in hazardous activities requiring mental alertness, such as operating motor vehicles or dangerous machinery, until the effect of FYCOMPA is known. Patients should be carefully observed for signs of central nervous system (CNS) depression, such as somnolence and sedation, when FYCOMPA is used with other drugs with sedative properties because of potential additive effects.

5.4 Falls

An increased risk of falls, in some cases leading to serious injuries including head injuries and bone fracture, occurred in patients being treated with FYCOMPA (with and without concurrent seizures). In the controlled partial-onset seizure clinical trials, falls were reported in 5% and 10% of patients randomized to receive FYCOMPA at doses of 8 mg and 12 mg per day, respectively, compared to 3% of placebo-treated patients. Falls were reported as serious and led to discontinuation more frequently in FYCOMPA-treated patients than placebo-treated patients. Elderly patients had an increased risk of falls compared to younger adults and pediatric patients.

5.5 Drug Reaction with Eosinophilia and Systemic Symptoms (DRESS)/Multiorgan Hypersensitivity

Drug Reaction with Eosinophilia and Systemic Symptoms (DRESS), also known as Multiorgan hypersensitivity, has been reported in patients taking antiepileptic drugs, including FYCOMPA. DRESS may be fatal or life-threatening. DRESS typically, although not exclusively, presents with fever, rash, lymphadenopathy, and/or facial swelling, in association with other organ system involvement, such as hepatitis, nephritis, hematological abnormalities, myocarditis, or myositis sometimes resembling an acute viral infection. Eosinophilia is often present. Because this disorder is variable in its expression, other organ systems not noted here may be involved. It is important to note that early manifestations of hypersensitivity, such as fever or lymphadenopathy, may be present even though rash is not evident. If such signs or symptoms are present, the patient should be evaluated immediately. FYCOMPA should be discontinued if an alternative etiology for the signs or symptoms cannot be established.

5.6 Withdrawal of Antiepileptic Drugs

There is the potential of increased seizure frequency in patients with seizure disorders when antiepileptic drugs are withdrawn abruptly. FYCOMPA has a half-life of approximately 105 hours so that even after abrupt cessation, blood levels fall gradually. In epilepsy clinical trials FYCOMPA was withdrawn without down-titration. Although a small number of patients exhibited seizures following discontinuation, the data were not sufficient to allow any recommendations regarding appropriate withdrawal regimens. A gradual withdrawal is generally recommended with antiepileptic drugs, but if withdrawal is a response to adverse events, prompt withdrawal can be considered.

6 ADVERSE REACTIONS

The following serious adverse reactions are described below and elsewhere in the labeling:

- Serious Psychiatric and Behavioral Reactions [see Warnings and Precautions (5.1)]
- Suicidal Behavior and Ideation [see Warnings and Precautions (5.2)]
- Neurologic Effects [see Warnings and Precautions (5.3)]
- Falls [see Warnings and Precautions (5.4)]
- Drug Reaction with Eosinophilia and Systemic Symptoms (DRESS)/Multiorgan Hypersensitivity [see Warnings and Precautions (5.5)]

6.1 Clinical Trials Experience

Because clinical trials are conducted under widely varying conditions, adverse reaction rates observed in the clinical trials of a drug cannot be directly compared to rates in the clinical trials of another drug and may not reflect the rates observed in clinical practice.

Partial-Onset Seizures

Adult and Adolescent Patients (12 years of age and older)

A total of 1,038 patients receiving FYCOMPA (2, 4, 8, or 12 mg once daily) constituted the safety population in the pooled analysis of the placebo-controlled trials (Studies 1, 2, and 3) in patients with partial-onset seizures. Approximately 51% of patients were female, and the mean age was 35 years.

Adverse Reactions Leading to Discontinuation

In controlled clinical trials (Studies 1, 2, and 3), the rate of discontinuation as a result of an adverse reaction was 3%, 8%, and 19% in patients randomized to receive FYCOMPA at the recommended doses of 4 mg, 8 mg, and 12 mg per day, respectively, and 5% in patients randomized to receive placebo [see Clinical Studies (14)]. The adverse reactions most commonly leading to discontinuation (≥1% in the 8 mg or 12 mg FYCOMPA group and greater than placebo) were dizziness, somnolence, vertigo, aggression, anger, ataxia, blurred vision, irritability, and dysarthria [see Warnings and Precautions (5.1, 5.3)].

Most Common Adverse Reactions

Table 2 gives the incidence in the controlled clinical trials (Studies 1, 2, and 3) of the adverse reactions that occurred in ≥2% of patients with partial-onset seizures in the FYCOMPA 12 mg dose group and more frequent than placebo (in order of decreasing frequency for the 12 mg dose group).

The most common dose-related adverse reactions in patients receiving FYCOMPA at doses of 8 mg or 12 mg (≥4% and occurring at least 1% higher than the placebo group) included dizziness (36%), somnolence (16%), fatigue (10%), irritability (9%), falls (7%), nausea (7%), ataxia (5%), balance disorder (4%), gait disturbance (4%), vertigo (4%), and weight gain (4%). For almost every adverse reaction, rates were higher on 12 mg and more often led to dose reduction or discontinuation.

Table 2. Adverse Reactions in Pooled Placebo-Controlled Trials in Adult and Adolescent Patients with Partial-Onset Seizures (Studies 1, 2, and 3) (Reactions ≥2% of Patients in Highest FYCOMPA Dose (12 mg) Group and More Frequent than Placebo)
 | Placebo; n=442; % | FYCOMPA
 | Placebo; n=442; % | 4 mg; n=172; % | 8 mg; n=431; % | 12 mg; n=255; %
Dizziness | 9 | 16 | 32 | 43
Somnolence | 7 | 9 | 16 | 18
Headache | 11 | 11 | 11 | 13
Irritability | 3 | 4 | 7 | 12
Fatigue | 5 | 8 | 8 | 12
Falls | 3 | 2 | 5 | 10
Ataxia | 0 | 1 | 3 | 8
Nausea | 5 | 3 | 6 | 8
Vertigo | 1 | 4 | 3 | 5
Back pain | 2 | 2 | 2 | 5
Dysarthria | 0 | 1 | 3 | 4
Anxiety | 1 | 2 | 3 | 4
Blurred vision | 1 | 1 | 3 | 4
Gait disturbance | 1 | 1 | 4 | 4
Weight gain | 1 | 4 | 4 | 4
Cough | 3 | 1 | 1 | 4
Upper respiratory tract infection | 3 | 3 | 3 | 4
Vomiting | 3 | 2 | 3 | 4
Hypersomnia | 0 | 1 | 2 | 3
Anger | <1 | 0 | 1 | 3
Aggression | 1 | 1 | 2 | 3
Balance disorder | 1 | 0 | 5 | 3
Diplopia | 1 | 1 | 1 | 3
Head injury | 1 | 1 | 1 | 3
Hypoaesthesia | 1 | 0 | 0 | 3
Pain in extremity | 1 | 0 | 2 | 3
Constipation | 2 | 2 | 2 | 3
Myalgia | 2 | 1 | 1 | 3
Coordination abnormal | 0 | 1 | <1 | 2
Euphoric mood | 0 | 0 | <1 | 2
Confusional state | <1 | 1 | 1 | 2
Hyponatremia | <1 | 0 | 0 | 2
Limb injury | <1 | 1 | 1 | 2
Mood altered | <1 | 1 | <1 | 2
Arthralgia | 1 | 0 | 3 | 2
Asthenia | 1 | 1 | 2 | 2
Contusion | 1 | 0 | 2 | 2
Memory impairment | 1 | 0 | 1 | 2
Musculoskeletal pain | 1 | 1 | 1 | 2
Oropharyngeal pain | 1 | 2 | 2 | 2
Paraesthesia | 1 | 0 | 1 | 2
Peripheral edema | 1 | 1 | 1 | 2
Skin laceration | 1 | 0 | 2 | 2

Pediatric Patients (4 to <12 years of age)

In two studies in pediatric patients 4 to <12 years of age with epilepsy, a total of 225 patients received FYCOMPA, with 110 patients exposed for at least 6 months, and 21 patients for at least 1 year. Adverse reactions in pediatric patients 4 to <12 years of age were similar to those seen in patients 12 years of age and older.

Primary Generalized Tonic-Clonic Seizures

A total of 81 patients receiving FYCOMPA 8 mg once daily constituted the safety population in the placebo-controlled trial in patients with primary generalized tonic-clonic seizures (Study 4). Approximately 57% of patients were female, and the mean age was 27 years.

In the controlled primary generalized tonic-clonic seizure clinical trial (Study 4), the adverse reaction profile was similar to that noted for the controlled partial-onset seizure clinical trials (Studies 1, 2, and 3).

Table 3 gives the incidence of adverse reactions in patients receiving FYCOMPA 8 mg (≥4% and higher than in the placebo group) in Study 4. The most common adverse reactions in patients receiving FYCOMPA (≥10% and greater than placebo) were dizziness (32%), fatigue (15%), headache (12%), somnolence (11%), and irritability (11%).

The adverse reactions most commonly leading to discontinuation in patients receiving FYCOMPA 8 mg (≥2% and greater than placebo) were vomiting (2%) and dizziness (2%).

Table 3. Adverse Reactions in a Placebo-Controlled Trial in Patients with Primary Generalized Tonic-Clonic Seizures (Study 4) (Reactions ≥4% of Patients in FYCOMPA Group and More Frequent than Placebo)
 | Placebo; n=82; % | FYCOMPA 8 mg; n=81; %
Dizziness | 6 | 32
Fatigue | 6 | 15
Headache | 10 | 12
Somnolence | 4 | 11
Irritability | 2 | 11
Vertigo | 2 | 9
Vomiting | 2 | 9
Weight gain | 4 | 7
Contusion | 4 | 6
Nausea | 5 | 6
Abdominal pain | 1 | 5
Anxiety | 4 | 5
Urinary tract infection | 1 | 4
Ligament sprain | 0 | 4
Balance disorder | 1 | 4
Rash | 1 | 4

Weight Gain

Weight gain has occurred with FYCOMPA.

In controlled partial-onset seizure clinical trials, FYCOMPA-treated adults gained an average of 1.1 kg (2.5 lbs) compared to an average of 0.3 kg (0.7 lbs) in placebo-treated adults with a median exposure of 19 weeks. The percentages of adults who gained at least 7% and 15% of their baseline body weight in FYCOMPA-treated patients were 9.1% and 0.9%, respectively, as compared to 4.5% and 0.2% of placebo-treated patients, respectively. Clinical monitoring of weight is recommended.

Similar increases in weight were also observed in adult and adolescent patients treated with FYCOMPA in the primary generalized tonic-clonic seizure clinical trial.

Elevated triglycerides

Increases in triglycerides have occurred with FYCOMPA use.

Comparison of Sex and Race

No significant sex differences were noted in the incidence of adverse reactions.

Although there were few non-Caucasian patients, no differences in the incidence of adverse reactions compared to Caucasian patients were observed.

6.2 Postmarketing Experience

The following adverse reactions have been identified during post approval use of FYCOMPA. Because these reactions are reported voluntarily from a population of uncertain size, it is not always possible to reliably estimate their frequency or establish a causal relationship to drug exposure.

Dermatologic: Drug Reaction with Eosinophilia and Systemic Symptoms (DRESS) [see Warnings and Precautions (5.5)]

Psychiatric: Acute psychosis, hallucinations, delusions, paranoia, delirium, confusional state, disorientation, memory impairment [see Warnings and Precautions (5.1)].

7 DRUG INTERACTIONS

7.1 Contraceptives

With concomitant use, FYCOMPA at a dose of 12 mg per day reduced levonorgestrel exposure by approximately 40% [see Clinical Pharmacology (12.3)]. Use of FYCOMPA with contraceptives containing levonorgestrel may render them less effective. Additional non-hormonal forms of contraception are recommended [see Use in Specific Populations (8.3)].

7.2 Moderate and Strong CYP3A4 Inducers

The concomitant use of known moderate and strong CYP3A4 inducers including carbamazepine, phenytoin, or oxcarbazepine with FYCOMPA decreased the plasma levels of perampanel by approximately 50-67% [see Clinical Pharmacology (12.3)]. The starting doses for FYCOMPA should be increased in the presence of moderate or strong CYP3A4 inducers [see Dosage and Administration (2.3)].

When these moderate or strong CYP3A4 inducers are introduced or withdrawn from a patient’s treatment regimen, the patient should be closely monitored for clinical response and tolerability. Dose adjustment of FYCOMPA may be necessary [see Dosage and Administration (2.3)].

7.3 Alcohol and Other CNS Depressants

The concomitant use of FYCOMPA and CNS depressants including alcohol may increase CNS depression. A pharmacodynamic interaction study in healthy subjects found that the effects of FYCOMPA on complex tasks such as driving ability were additive or supra-additive to the impairment effects of alcohol [see Clinical Pharmacology (12.3)]. Multiple dosing of FYCOMPA 12 mg per day also enhanced the effects of alcohol to interfere with vigilance and alertness, and increased levels of anger, confusion, and depression. These effects may also be seen when FYCOMPA is used in combination with other CNS depressants. Care should be taken when administering FYCOMPA with these agents. Patients should limit activity until they have experience with concomitant use of CNS depressants (e.g., benzodiazepines, narcotics, barbiturates, sedating antihistamines). Advise patients not to drive or operate machinery until they have gained sufficient experience on FYCOMPA to gauge whether it adversely affects these activities.

8 USE IN SPECIFIC POPULATIONS

8.1 Pregnancy

Pregnancy Exposure Registry

There is a pregnancy exposure registry that monitors pregnancy outcomes in women exposed to antiepileptic drugs (AEDs), such as FYCOMPA, during pregnancy. Encourage women who are taking FYCOMPA during pregnancy to enroll in the North American Antiepileptic Drug (NAAED) Pregnancy Registry by calling 1-888-233-2334 or visiting http://www.aedpregnancyregistry.org.

Risk Summary

There are no adequate data on the developmental risk associated with use in pregnant women. In animal studies, perampanel induced developmental toxicity in pregnant rat and rabbit at clinically relevant doses [see Data]. In the U.S. general population the estimated background risk of major birth defects and miscarriage in clinically recognized pregnancies is 2-4% and 15-20%, respectively. The background risk of major birth defects and miscarriage for the indicated population is unknown.

Data

Animal Data

Oral administration of perampanel (1, 3, or 10 mg/kg/day) to pregnant rats throughout organogenesis resulted in an increase in visceral abnormalities (diverticulum of the intestine) at all doses tested; maternal toxicity was observed at the mid and high doses. In a dose-ranging study at higher oral doses (10, 30, or 60 mg/kg/day), embryo lethality and reduced fetal body weight were observed at the mid and high doses tested. The lowest dose tested (1 mg/kg/day) is similar to a human dose of 8 mg/day based on body surface area (mg/m^2).

Upon oral administration of perampanel (1, 3, or 10 mg/kg/day) to pregnant rabbits throughout organogenesis, embryo lethality and maternal toxicity were observed at the mid and high doses tested; the no-effect dose for embryo-fetal developmental toxicity in rabbit (1 mg/kg/day) is approximately 2 times a human dose of 8 mg/day based on body surface area (mg/m^2).

Oral administration of perampanel (1, 3, or 10 mg/kg/day) to rats throughout gestation and lactation resulted in fetal and pup deaths at the mid and high doses (associated with maternal toxicity) and delayed sexual maturation in males and females at the highest dose tested. No effects were observed on measures of neurobehavioral or reproductive function in the offspring. The no-effect dose for pre- and postnatal developmental toxicity in rat (1 mg/kg/day) is similar to a human dose of 8 mg/day based on body surface area (mg/m^2).

8.2 Lactation

Risk Summary

There are no data on the presence of perampanel in human milk, the effects on the breastfed child, or the effects of the drug on milk production. Perampanel and/or its metabolites are present in rat milk, and are detected at concentrations higher than that in maternal plasma.

The developmental and health benefits of breastfeeding should be considered along with the mother’s clinical need for FYCOMPA and any potential adverse effects on the breastfed child from FYCOMPA or from the underlying maternal condition.

8.3 Females and Males of Reproductive Potential

Contraception

Use of FYCOMPA may reduce the efficacy of hormonal contraceptives containing levonorgestrel. Advise women taking FYCOMPA who are using a levonorgestrel-containing contraceptive to use an additional non-hormonal form of contraception while using FYCOMPA and for a month after discontinuation [see Drug Interactions (7.1), Clinical Pharmacology (12.3)].

8.4 Pediatric Use

Safety and effectiveness of FYCOMPA for the treatment of partial-onset seizures have been established in pediatric patients 4 years of age and older.

The safety and effectiveness of FYCOMPA in patients 12 years of age and older was established by three randomized double-blind, placebo-controlled, multicenter studies, which included 72 pediatric patients between 12 and 16 years of age exposed to FYCOMPA [see Clinical Pharmacology (12.3) and Clinical Studies (14.1)]. Use of FYCOMPA for the treatment of partial-onset seizures in pediatric patients 4 years to less than 12 years of age is supported by evidence from adequate and well-controlled studies of FYCOMPA in patients 12 years of age and older with partial onset seizures, pharmacokinetic data from adult and pediatric patients, and safety data in 225 pediatric patients 4 years to less than 12 years of age treated with FYCOMPA [see Adverse Reactions (6.1) and Clinical Pharmacology (12.3)].

The safety and efficacy of FYCOMPA for the adjunctive therapy of primary generalized tonic-clonic seizures in pediatric patients 12 years of age and older was established in a single randomized double-blind, placebo-controlled, multicenter trial (n=164), which included 11 pediatric patients 12 to 16 years of age exposed to FYCOMPA; an additional 6 patients were treated with FYCOMPA in the open-label extension of the study [see Clinical Studies (14.2)].

The safety and effectiveness of FYCOMPA for the treatment of partial-onset seizures in pediatric patients less than 4 years of age or for the treatment of primary generalized tonic-clonic seizures in pediatric patients less than 12 years of age have not been established.

Juvenile Animal Data

Oral administration of perampanel (1, 3, 3/10/30 mg/kg/day; high dose increased on postnatal days [PND] 28 and 56) to young rats for 12 weeks starting on PND 7 resulted in reduced body weight, reduced growth, neurobehavioral impairment (water maze performance and auditory startle habituation) at the mid and high doses, and delayed sexual maturation at the high doses. CNS signs (reduced activity, incoordination, excessive grooming/scratching), pup death, decreased hindlimb splay, and decreased hindlimb grip strength were observed at all doses. Effects on pup body weight, pup growth, hindlimb splay, impairment in the water maze performance, and auditory startle persisted after dosing was stopped. A no-effect dose for postnatal developmental toxicity was not identified in this study.

Oral administration of perampanel (1, 5, 5/10 mg/kg/day; high dose increased on PND 56) to juvenile dogs for 33 weeks, starting on PND 42, resulted in CNS signs (incoordination, excessive grooming/licking/scratching, spatial disorientation, and/or ataxic gait) at all doses tested.

8.5 Geriatric Use

Clinical studies of FYCOMPA did not include sufficient numbers of patients aged 65 and over to determine the safety and efficacy of FYCOMPA in the elderly population. Because of increased likelihood for adverse reactions in the elderly, dosing titration should proceed slowly in patients aged 65 years and older [see Dosage and Administration (2.5)].

8.6 Hepatic Impairment

Use of FYCOMPA in patients with severe hepatic impairment is not recommended, and dosage adjustments are recommended in patients with mild or moderate hepatic impairment [see Dosage and Administration (2.4), Clinical Pharmacology (12.3)].

8.7 Renal Impairment

Dose adjustment is not required in patients with mild renal impairment. FYCOMPA should be used with caution in patients with moderate renal impairment, and slower titration may be considered. Use in patients with severe renal impairment or patients undergoing hemodialysis is not recommended [see Dosage and Administration (2.5), Clinical Pharmacology (12.3)].

9 DRUG ABUSE AND DEPENDENCE

9.1 Controlled Substance

FYCOMPA contains perampanel and is listed as a Schedule III controlled substance.

9.2 Abuse

Prescription drug abuse is the intentional non-therapeutic use of a drug, even once, for its rewarding psychological or physiological effects. Drug addiction, which develops after repeated drug abuse, is characterized by a strong desire to take a drug despite harmful consequences, difficulty in controlling its use, giving a higher priority to drug use than to obligations, increased tolerance, and sometimes physical withdrawal. Drug abuse and drug addiction are separate and distinct from physical dependence (for example, abuse may not be accompanied by physical dependence) [see Drug Abuse and Dependence (9.3)].

Studies of human abuse potential were performed to evaluate the abuse potential of FYCOMPA (8 mg, 24 mg, and 36 mg) as compared to alprazolam C-IV (1.5 mg and 3 mg), and oral ketamine C-III (100 mg) in recreational polydrug users. Supra-therapeutic doses of FYCOMPA 24 and 36 mg produced responses for “Euphoria” that were similar to ketamine 100 mg and alprazolam 3 mg. For “High,” FYCOMPA 24 mg and 36 mg produced responses comparable to ketamine 100 mg and significantly higher than both doses of alprazolam on a visual analog scale (VAS). “Drug Liking,” “Overall Drug Liking,” and “Take Drug Again” for FYCOMPA were each statistically lower than ketamine 100 mg. In addition, for “Bad Drug Effects,” FYCOMPA 24 mg and 36 mg produced responses significantly higher than ketamine 100 mg. For “Sedation,” FYCOMPA 24 and 36 mg produced responses similar to alprazolam 3 mg and higher than ketamine 100 mg.

Additionally, on VAS measures related to dissociative phenomena such as “Floating,” “Spaced Out,” and “Detached,” FYCOMPA at supratherapeutic doses produced responses similar to ketamine 100 mg and greater than both doses of alprazolam tested. Of note, due to somnolence a number of subjects had missing data around Tmax of FYCOMPA. The above described data might represent an underestimate of FYCOMPA’s effects. The duration of effects of higher doses of FYCOMPA on the majority of measures was much greater than alprazolam 3 mg and ketamine 100 mg.

In this study, the incidence of euphoria following FYCOMPA administration 8 mg, 24 mg, and 36 mg was 37%, 46%, 46%, respectively, which was higher than alprazolam 3 mg (13%) but lower than ketamine 100 mg (89%).

9.3 Dependence

Physical dependence is characterized by withdrawal symptoms after abrupt discontinuation or a significant dose reduction of a drug.

A nonclinical dependence study in rats demonstrated withdrawal symptoms, including hyperreactivity to handling, muscle rigidity, and decreases in food consumption and body weights.

FYCOMPA may cause dependence and withdrawal symptoms that may include anxiety, nervousness, irritability, fatigue, lethargy, asthenia, mood swings, and insomnia.

10 OVERDOSAGE

The highest reported overdose of FYCOMPA was 300 mg. Events reported after FYCOMPA overdose include somnolence, stupor, coma, psychiatric or behavioral reactions, altered mental status, and dizziness or gait disturbances.

There is no available specific antidote to the overdose reactions of FYCOMPA. In the event of overdose, standard medical practice for the management of any overdose should be used. An adequate airway, oxygenation, and ventilation should be ensured; monitoring of cardiac rhythm and vital sign measurement is recommended. A certified poison control center should be contacted for updated information on the management of overdose with FYCOMPA. Due to its long half-life, the reactions caused by FYCOMPA could be prolonged.

11 DESCRIPTION

FYCOMPA tablets and oral suspension contain perampanel, a non-competitive AMPA receptor antagonist, as a 4:3 hydrate.

The chemical name of the active ingredient is 2-(1′,6′-dihydro-6′-oxo-1′-phenyl[2,3′-bipyridin]-5′-yl)-benzonitrile, hydrate (4:3).

The molecular formula is C23H15N3O • ¾H2O and the molecular weight is 362.90 (349.39 for anhydrous perampanel). It is a white to yellowish white powder. It is freely soluble in 1-methyl-2-pyrrolidinone, sparingly soluble in acetonitrile and acetone, slightly soluble in methanol, ethanol and ethyl acetate, very slightly soluble in 1-octanol and diethyl ether, and practically insoluble in heptane and water. The chemical structure is:

Tablets

FYCOMPA tablets are round, bi-convex, film-coated tablets containing 2 mg, 4 mg, 6 mg, 8 mg, 10 mg, or 12 mg of perampanel. Tablets contain the following inactive ingredients: lactose monohydrate, low substituted hydroxypropyl cellulose, povidone, microcrystalline cellulose, magnesium stearate, hypromellose, polyethylene glycol, talc, and titanium dioxide. Tablets of different strengths may contain yellow ferric oxide (10 mg and 2 mg), red ferric oxide (2 mg, 4 mg, 6 mg, 8 mg), black ferric oxide (8 mg), and FD&C Blue No. 2 (indigo carmine) aluminum lake (10 mg and 12 mg).

Oral Suspension

FYCOMPA oral suspension is a white to off-white opaque liquid providing perampanel in a concentration of 0.5 mg/mL. The oral suspension contains the following inactive ingredients: sorbitol, microcrystalline cellulose, carboxymethyl-cellulose sodium, poloxamer, simethicone, citric acid, sodium benzoate and purified water.

12 CLINICAL PHARMACOLOGY

12.1 Mechanism of Action

Perampanel is a non-competitive antagonist of the ionotropic α-amino-3-hydroxy-5-methyl-4-isoxazolepropionic acid (AMPA) glutamate receptor on post-synaptic neurons. Glutamate is the primary excitatory neurotransmitter in the central nervous system and is implicated in a number of neurological disorders caused by neuronal over excitation.

The precise mechanism by which FYCOMPA exerts its antiepileptic effects in humans is unknown.

12.2 Pharmacodynamics

Psychomotor Performance

In a healthy volunteer study to assess the effects of FYCOMPA tablets on psychomotor performance using a standard battery of assessments including simulated driving, single and multiple daily doses of FYCOMPA 4 mg did not impair simple psychomotor tasks, driving performance, or sensorimotor coordination. Single and multiple doses of 8 mg and 12 mg impaired psychomotor performance in a dose-related manner. Car handling ability was impaired after dosing of FYCOMPA 12 mg, but postural stability was not significantly impaired. Performance testing returned to baseline within 2 weeks of cessation of FYCOMPA dosing.

Interactions with Alcohol

In the above study (see Psychomotor Performance), when administered to healthy subjects receiving alcohol to achieve a blood concentration of 80-100 mg/100 mL, FYCOMPA consistently impaired simple psychomotor performance after single doses of 4 to 12 mg, and after 21 days of multiple 12 mg/day doses. The effects of FYCOMPA on complex tasks such as driving ability were additive or supra-additive to the impairment effects of alcohol. FYCOMPA enhanced the effects of alcohol on vigilance and alertness, and increased levels of anger, confusion, and depression.

Potential to Prolong QT Interval

In a placebo-controlled thorough QT study of perampanel in healthy subjects, there was no evidence that perampanel caused QT interval prolongation of clinical significance at doses of 6 or 12 mg (i.e., the upper bound of the 95% confidence interval for the largest placebo-adjusted baseline-corrected QTc was below 10 msec). The exposures observed with the 12 mg dose in this study will not cover the exposures expected in patients with hepatic impairment taking doses over 6 mg/day. At the highest recommended dose (12 mg), perampanel did not prolong the QTc interval to any clinically relevant extent.

12.3 Pharmacokinetics

Pharmacokinetics of perampanel are similar in healthy subjects, patients with partial-onset seizures, and patients with primary generalized tonic-clonic seizures. The half-life of perampanel is about 105 hours, so that steady state is reached in about 2-3 weeks. AUC of perampanel increased in a dose-proportional manner after single-dose administration of 0.2-12 mg tablets and after multiple-dose administration of 1-12 mg tablets once daily.

FYCOMPA oral suspension has comparable bioavailability to FYCOMPA tablets under steady state. Both formulations may be used interchangeably.

The pharmacokinetics of perampanel are similar when used as monotherapy or as adjunctive therapy for the treatment of partial-onset seizures (in the absence of concomitant moderate or strong CYP3A4 inducers).

Absorption

Perampanel is rapidly and completely absorbed after oral administration with negligible first-pass metabolism. Median time to reach peak concentration (tmax) ranged from 0.5 to 2.5 hours under fasted condition. Co-administration of FYCOMPA tablet with a high fat meal had no impact on the total exposure (AUC0-inf) of perampanel and reduced the peak plasma concentration (Cmax) of perampanel by 11%-40%. The tmax was delayed by approximately 1-3 hours in fed state compared to that under fasted conditions.

Distribution

Data from in vitro studies indicate that, in the concentration range of 20 to 2000 ng/mL, perampanel is approximately 95-96% bound to plasma proteins, mainly bound to albumin and α1-acid glycoprotein. Blood to plasma ratio of perampanel is 0.55-0.59.

Metabolism

Perampanel is extensively metabolized via primary oxidation and sequential glucuronidation. Oxidative metabolism is primarily mediated by CYP3A4/5 and to a lesser extent by CYP1A2 and CYP2B6, based on results of in vitro studies using recombinant human CYPs and human liver microsomes. Other CYP enzymes may also be involved.

Following administration of radiolabeled perampanel, unchanged perampanel accounted for 74-80% of total radioactivity in systemic circulation, whereas only trace amounts of individual perampanel metabolites were detected in plasma.

Elimination

Following administration of a radiolabeled perampanel tablet dose to 8 healthy elderly subjects, 22% of administered radioactivity was recovered in the urine and 48% in the feces. In urine and feces, recovered radioactivity was primarily composed of a mixture of oxidative and conjugated metabolites. Population pharmacokinetic analysis of pooled data from 19 Phase 1 studies reported that t1/2 of perampanel was 105 hours on average. Apparent clearance of perampanel in healthy subjects and patients was approximately 12 mL/min.

Specific Populations

Hepatic Impairment

The pharmacokinetics of perampanel following a single 1 mg tablet dose were evaluated in 12 subjects with mild and moderate hepatic impairment (Child-Pugh A and B, respectively) compared with 12 demographically matched healthy subjects. The total (free and protein bound) exposure (AUC0-inf) of perampanel was 50% greater in subjects with mild hepatic impairment and more than doubled (2.55-fold) in subjects with moderate hepatic impairment compared to their healthy controls. The AUC0-inf of free perampanel in subjects with mild and moderate hepatic impairment was 1.8-fold and 3.3-fold, respectively, of those in matched healthy controls. The t1/2 was prolonged in subjects with mild impairment (306 vs. 125 hours) and moderate impairment (295 vs. 139 hours). Perampanel has not been studied in subjects with severe hepatic impairment [see Dosage and Administration (2.4), Use in Specific Populations (8.6)].

Renal Impairment

A dedicated study has not been conducted to evaluate the pharmacokinetics of perampanel in patients with renal impairment. Population pharmacokinetic analysis was performed on pooled data from patients with partial-onset seizures and receiving FYCOMPA tablets up to 12 mg/day in placebo-controlled clinical trials. Results showed that perampanel apparent clearance was decreased by 27% in patients with mild renal impairment (creatinine clearance 50-80 mL/min) compared to patients with normal renal function (creatinine clearance >80 mL/min), with a corresponding 37% increase in AUC. Considering the substantial overlap in the exposure between normal and mildly impaired patients, no dosage adjustment is necessary for patients with mild renal impairment. Perampanel has not been studied in patients with severe renal impairment and patients undergoing hemodialysis [see Dosage and Administration (2.5), Use in Specific Populations (8.7)].

Sex

In a population pharmacokinetic analysis of patients with partial-onset and primary generalized tonic-clonic seizures receiving FYCOMPA tablets in placebo-controlled clinical trials, perampanel apparent clearance in females (0.54 L/hr) was 18% lower than in males (0.66 L/hr). No dosage adjustment is necessary based on sex.

Pediatrics

In a population pharmacokinetic analysis of healthy subjects and pediatric and adult patients with partial onset seizures, including 123 children 4 years to less than 12 years of age, 226 adolescents 12 years to less than 18 years of age, and 1912 adults 18 years of age and older, no significant effect of age or body weight on perampanel clearance was found.

Geriatrics

In a population pharmacokinetic analysis of patients with partial-onset seizures and primary generalized tonic-clonic seizures ranging in age from 12 to 74 years receiving FYCOMPA tablets in placebo-controlled trials, no significant effect of age on perampanel apparent clearance was found [see Dosage and Administration (2.6), Use in Specific Populations (8.5)].

Race

In a population pharmacokinetic analysis of patients with partial-onset seizures and primary generalized tonic-clonic seizures, which included 614 Caucasians, 15 Blacks, 4 Japanese, 4 American Indians/Alaska Natives, 79 Chinese and 108 other Asians receiving FYCOMPA tablets in placebo-controlled trials, no significant effect of race on perampanel apparent clearance was found. No dosage adjustment is necessary.

Drug Interaction Studies

In Vitro Assessment of Drug Interactions

Drug Metabolizing Enzymes

In human liver microsomes, perampanel at a concentration of 30 μmol/L, about 10 fold the steady state Cmax at a 12 mg dose, had a weak inhibitory effect on CYP2C8, CYP3A4, UGT1A9, and UGT2B7. Perampanel did not inhibit CYP1A2, CYP2A6, CYP2B6, CYP2C9, CYP2C19, CYP2D6, CYP2E1, UGT1A1, UGT1A4, and UGT1A6 up to a concentration of 30 µmol/L.

Compared with positive controls (including phenobarbital and rifampin), perampanel was found to weakly induce CYP2B6 (30 µmol/L) and CYP3A4/5 (≥3 µmol/L) in cultured human hepatocytes. Perampanel also induced UGT1A1 (≥3 µmol/L) and UGT1A4 (30 µmol/L). Perampanel did not induce CYP1A2 at concentrations up to 30 µmol/L.

Transporters

In vitro studies showed that perampanel is not a substrate or significant inhibitor of the following: organic anion transporting polypeptides 1B1 and 1B3; organic anion transporters 1, 2, 3, and 4; organic cation transporters 1, 2, and 3; efflux transporters P-glycoprotein and Breast Cancer Resistance Protein.

In Vivo Assessment of Drug Interactions

Drug Interactions with AEDs

Effect of Concomitant AEDs on FYCOMPA:

Carbamazepine. As an inducer of CYP enzymes, carbamazepine increases perampanel clearance. Steady state administration of carbamazepine at 300 mg BID in healthy subjects reduced the Cmax and AUC0-inf of a single 2 mg tablet dose of perampanel by 26% and 67%, respectively. The t1/2 of perampanel was shortened from 56.8 hours to 25 hours. In clinical studies examining partial-onset and primary generalized tonic-clonic seizures, a population pharmacokinetic analysis showed that perampanel AUC was reduced by 64% in patients on carbamazepine compared to the AUC in patients not on enzyme-inducing AEDs [see Dosage and Administration (2.3), Drug Interactions (7.2)].

Oxcarbazepine. In clinical studies examining partial-onset and primary generalized tonic-clonic seizures, a population pharmacokinetic analysis showed that perampanel AUC was reduced by 48% in patients on oxcarbazepine compared to patients not on enzyme-inducing AEDs [see Dosage and Administration (2.3), Drug Interactions (7.2)].

Eslicarbazepine. Eslicarbazepine is structurally similar to oxcarbazepine and thus may also reduce perampanel plasma concentrations when used concomitantly.

Phenytoin. In clinical studies examining partial-onset and primary generalized tonic-clonic seizures, a population pharmacokinetic analysis showed that perampanel AUC was reduced by 43% in patients on phenytoin compared to patients not on enzyme-inducing AEDs [see Dosage and Administration (2.3), Drug Interactions (7.2)].

Phenobarbital and Primidone: In a population pharmacokinetic analysis of patients with partial-onset and primary generalized tonic-clonic seizures in clinical trials (40 patients co-administered phenobarbital and 9 patients co-administered primidone), no significant effect on perampanel AUC was found. A modest effect of phenobarbital and primidone on perampanel concentrations cannot be excluded.

Topiramate: Population pharmacokinetic analysis of patients with partial-onset and primary generalized tonic-clonic seizures in clinical trials showed that perampanel AUC was reduced by approximately 19% in patients on topiramate compared to patients not on enzyme-inducing AEDs.

Other AEDs: Population pharmacokinetic analysis of patients with partial-onset and primary generalized tonic-clonic seizures in clinical trials showed that clobazam, clonazepam, lamotrigine, levetiracetam, valproate, and zonisamide did not have an effect on perampanel clearance.

Other strong CYP3A inducers (e.g., rifampin, St. John’s wort) may also greatly increase clearance of perampanel and reduce perampanel plasma concentrations [see Drug Interactions (7.2)].

Effect of FYCOMPA on Concomitant AEDs:

FYCOMPA tablets up to 12 mg/day did not significantly affect the clearance of clonazepam, levetiracetam, phenobarbital, phenytoin, topiramate, or zonisamide based on a population pharmacokinetic analysis of patients with partial-onset seizures in clinical trials. FYCOMPA had a statistically significant effect on the clearance of carbamazepine, clobazam, lamotrigine, and valproic acid, but the increases in clearance of these drugs were each less than 10% at the highest perampanel dose evaluated (12 mg/day). FYCOMPA co-administration resulted in a 26% decrease in oxcarbazepine clearance and increased its concentrations. The concentrations of 10-monohydroxy metabolite (MHD), the active metabolite of oxcarbazepine, were not measured.

Drug-drug Interaction Studies with Other Drugs

Effect of Other Drugs on FYCOMPA

Ketoconazole. Co-administration of single 1-mg dose of perampanel tablet with 400 mg once daily doses of ketoconazole, a strong CYP3A4 inhibitor, for 8 days in healthy subjects prolonged perampanel t1/2 by 15% (67.8 vs. 58.4 hours) and increased AUC0-inf by 20%.

Contraceptives. Perampanel Cmax and AUC0-72h were not altered when a single 6-mg dose of perampanel tablet was administered to healthy female subjects following a 21-day course of oral contraceptives containing ethinylestradiol 30 µg and levonorgestrel 150 µg.

Effect of FYCOMPA on Other Drugs

Midazolam. Perampanel administered as 6 mg tablet once daily doses for 20 days decreased AUC0-inf and Cmax of midazolam (a CYP3A4 substrate) by 13% and 15%, respectively, in healthy subjects.

Contraceptives. Co-administration of perampanel 4 mg tablet once daily with an oral contraceptive containing ethinylestradiol 30 µg and levonorgestrel 150 µg for 21 days did not alter Cmax or AUC0-24h of either ethinylestradiol or levonorgestrel in healthy female subjects. In another study, a single dose of the oral contraceptive was administered following 21-day once daily dosing of FYCOMPA 12 mg or 8 mg tablets in healthy females. FYCOMPA at 12 mg did not alter AUC0-24h of ethinylestradiol but decreased its Cmax by 18%, and also decreased Cmax and AUC0-24h of levonorgestrel by 42% and 40%, respectively. FYCOMPA at 8 mg did not have significant effect on Cmax or AUC0-24h of either ethinylestradiol or levonorgestrel, with a decrease in AUC0-24h of levonorgestrel (9% on average) [see Drug Interactions (7.1), Use in Specific Populations (8.3)].

Levodopa. Perampanel tablets administered as 4 mg once daily doses for 19 days had no effect on Cmax and AUC0-inf of levodopa in healthy subjects.

13 NONCLINICAL TOXICOLOGY

13.1 Carcinogenesis, Mutagenesis, and Impairment of Fertility

Carcinogenesis

Perampanel was administered orally to mice (1, 3, 10, or 30 mg/kg/day) and rats (10, 30, or 100 mg/kg/day in males; 3, 10, or 30 mg/kg/day in females) for up to 104 weeks. There was no evidence of drug-related tumors in either species. Plasma perampanel exposures (AUC) at the highest doses tested were less than that in humans dosed at 8 mg/day.

Mutagenesis

Perampanel was negative in the in vitro Ames and mouse lymphoma tk assays, and in the in vivo rat micronucleus assay.

Impairment of Fertility

In male and female rats administered perampanel (oral doses of 1, 10, or 30 mg/kg/day) prior to and throughout mating and continuing in females to gestation day 6, there were no clear effects on fertility. Prolonged and/or irregular estrus cycles were observed at all doses but particularly at the highest dose tested. Plasma perampanel exposures (AUC) at all doses were lower than that in humans dosed at 8 mg/day.

14 CLINICAL STUDIES

14.1 Partial-Onset Seizures

The efficacy of FYCOMPA in partial-onset seizures, with or without secondary generalization, was studied in patients who were not adequately controlled with 1 to 3 concomitant AEDs in 3 randomized, double-blind, placebo-controlled, multicenter trials (Studies 1, 2, and 3) in adult and pediatric patients (12 years of age and older). All trials had an initial 6-week Baseline Period, during which patients were required to have more than five seizures in order to be randomized. The Baseline Period was followed by a 19-week Treatment Period consisting of a 6-week Titration Phase and a 13-week Maintenance Phase. Patients in these 3 trials had a mean duration of epilepsy of approximately 21 years and a median baseline seizure frequency ranging from 9 to 14 seizures per 28 days. During the trials, more than 85% of patients were taking 2 to 3 concomitant AEDs with or without concurrent vagal nerve stimulation, and approximately 50% were on at least one AED known to induce CYP3A4, an enzyme critical to the metabolism of FYCOMPA (i.e., carbamazepine, oxcarbazepine, or phenytoin), resulting in a significant reduction in FYCOMPA’s serum concentration [see Drug Interactions (7.2), Clinical Pharmacology (12.3)].

Each study evaluated placebo and multiple FYCOMPA dosages (see Figure 1). During the Titration period in all 3 trials, patients on FYCOMPA received an initial 2 mg once daily dose, which was subsequently increased in weekly increments of 2 mg per day to the final dose. Patients experiencing intolerable adverse reactions were permitted to have their dose reduced to the previously tolerated dose.

The primary endpoint in Studies 1, 2, and 3 was the percent change in seizure frequency per 28 days during the Treatment Period as compared to the Baseline Period. The criterion for statistical significance was p<0.05. A statistically significant decrease in seizure rate was observed at doses of 4 to 12 mg per day. Dose response was apparent at 4 to 8 mg with little

additional reduction in frequency at 12 mg per day.

Figure 1. Median Percent Reduction in Seizure Frequency per 28 Days from Baseline to Treatment Period

Tables 4 and 5 present an analysis combining data from all 3 studies, grouping patients based upon whether or not concomitant enzyme-inducing AEDs (carbamazepine, oxcarbazepine, or phenytoin) were used. The analysis revealed a substantially reduced effect in the presence of inducers.

Table 4. Median Percent Reduction for Combined Studies (Study 1, 2 and 3) Based on the Presence or Absence of Concomitant Enzyme-Inducing AEDs (carbamazepine, oxcarbazepine, phenytoin)a
 | Without Enzyme-Inducing AEDs |  | With Enzyme-Inducing AEDs
 | Placebo; % | FYCOMPA; % | Placebo; % | FYCOMPA; %
 | Placebo; % | FYCOMPA; % | Placebo; % | FYCOMPA; %
2 mg/day | 16 | 23 | 14 | 16
4 mg/day | 16 | 22 | 14 | 33
8 mg/day | 19 | 45 | 12 | 24
12 mg/day | 19 | 54 | 9 | 22
a Patients from Latin American region are excluded because of a significant treatment-by-region interaction due to high placebo response

Table 5. Responder Rate for Combined Studies (Study 1, 2 and 3) Based on the Presence or Absence of Concomitant Enzyme-Inducing AEDs (carbamazepine, oxcarbazepine, phenytoin) a,b
 | Without Enzyme-Inducing AEDs |  | With Enzyme-Inducing AEDs
 | Placebo; % | FYCOMPA; % | Placebo; % | FYCOMPA; %
 | Placebo; % | FYCOMPA; % | Placebo; % | FYCOMPA; %
2 mg/day | 19 | 26 | 18 | 20
4 mg/day | 19 | 35 | 18 | 26
8 mg/day | 17 | 45 | 19 | 32
12 mg/day | 15 | 54 | 21 | 33
a Patients from Latin American region are excluded because of a significant treatment-by-region interaction due to high placebo response; b The proportion of patients with at least a 50% decrease in seizure frequency

Figure 2 shows the proportion of patients with different percent reductions during the maintenance phase over baseline across all three trials. Patients in whom the seizure frequency increased are shown at left as “worse.” Patients in whom the seizure frequency decreased are shown in the remaining four categories.

Figure 2. Proportion of Patients Exhibiting Different Percent Reductions During the Maintenance Phase Over Baseline Across All Three Trials.

The percentages of patients with a 50% or greater reduction in seizure frequency were 19%, 29%, 35%, 35% for placebo, 4, 8, and 12 mg, respectively.

14.2 Primary Generalized Tonic-Clonic (PGTC) Seizures

The efficacy of FYCOMPA as adjunctive therapy in patients 12 years of age and older with idiopathic generalized epilepsy experiencing primary generalized tonic-clonic seizures was established in one multicenter, randomized, double-blind, placebo-controlled study (Study 4), conducted at 78 sites in 16 countries. Eligible patients on a stable dose of 1 to 3 AEDs experiencing at least 3 primary generalized tonic-clonic seizures during the 8-week baseline period were randomized to either FYCOMPA or placebo. Efficacy was analyzed in 162 patients (FYCOMPA N=81, placebo N=81) who received medication and at least one post-treatment seizure assessment. Patients were titrated over 4 weeks up to a dose of 8 mg per day or the highest tolerated dose and treated for an additional 13 weeks on the last dose level achieved at the end of the titration period. The total treatment period was 17 weeks. Study drug was given once per day.

The primary endpoint was the percent change from baseline in primary generalized tonic-clonic seizure frequency per 28 days during the treatment period as compared to the baseline period. The criterion for statistical significance was p<0.05. Table 6 shows the results of this study. A statistically significant decrease in seizure rate was observed with FYCOMPA compared to placebo.

Table 6. Median Percent Reduction from Baseline in Primary Generalized Tonic-Clonic Seizure Frequency in Study 4
 | Placebo; (N=81) | FYCOMPA; 8 mg; (N=81)
Percent Reduction During Treatment | 38 | 76a
a P-value compared to placebo: <0.0001. Statistically significant as compared to placebo based on ANCOVA with treatment and pooled country as factors and the ranked baseline seizure frequency per 28 days as a covariate.

Figure 3 shows the proportion of patients with different percent reductions during the maintenance phase over baseline in primary generalized tonic-clonic seizure frequency. Patients in whom the seizure frequency increased are shown at left as “worse.” Patients in whom the seizure frequency decreased are shown in the remaining four categories.

Figure 3. Proportion of Patients Exhibiting Different Percent Reductions During the Maintenance Phase Over Baseline in Primary Generalized Tonic-Clonic Seizure Frequency.

16 HOW SUPPLIED/STORAGE AND HANDLING

16.1 How Supplied

FYCOMPA Tablets

- 2 mg are orange, round, biconvex, film-coated tablets debossed with “2” on one side and “Є 275” on the other. They are supplied as follows:

Bottles of 30 NDC 69616-272-30

Bottles of 90 NDC 69616-272-90

- 4 mg are red, round, biconvex, film-coated tablets debossed with “4” on one side and “Є 277” on the other. They are supplied as follows:

Bottles of 30 NDC 69616-274-30

Bottles of 90 NDC 69616-274-90

- 6 mg are pink, round, biconvex, film-coated tablets debossed with “6” on one side and “Є 294” on the other. They are supplied as follows:

Bottles of 30 NDC 69616-276-30

Bottles of 90 NDC 69616-276-90

- 8 mg are purple, round, biconvex, film-coated tablets debossed with “8” on one side and “Є 295” on the other. They are supplied as follows:

Bottles of 30 NDC 69616-278-30

Bottles of 90 NDC 69616-278-90

- 10 mg are green, round, biconvex, film-coated tablets debossed with “10” on one side and “Є 296” on the other. They are supplied as follows:

Bottles of 30 NDC 69616-280-30

Bottles of 90 NDC 69616-280-90

- 12 mg are blue, round, biconvex, film-coated tablets debossed with “12” on one side and “Є 297” on the other. They are supplied as follows:

Bottles of 30 NDC 69616-282-30

Bottles of 90 NDC 69616-282-90

FYCOMPA Oral Suspension

- 0.5 mg/mL is a white to off-white opaque liquid. It is supplied in a round amber PET bottle with a child-resistant closure. It is packaged with a dispenser set that provides two 20-mL graduated oral dosing syringes and a push-in bottle adapter.
- Bottle containing 340 mL NDC 69616-290-38

16.2 Storage

Tablets: store at 20°C to 25°C (68°F to 77°F); excursions permitted to 15°C to 30°C (59°F to 86°F). [See USP Controlled Room Temperature]

Oral Suspension: Do not store above 30°C (86°F). Do not freeze. Use within 90 days after the first opening of the bottle.

17 PATIENT COUNSELING INFORMATION

Advise the patient to read the FDA-approved patient labeling (Medication Guide and Instructions for Use).

Administration of Oral Suspension

Advise patients who are prescribed the oral suspension to shake the bottle well before every administration and to use the adaptor and oral dosing syringe provided. Advise patients that a household teaspoon or tablespoon is not an adequate measuring device. Instruct patients to discard any unused FYCOMPA oral suspension remaining 90 days after first opening the bottle [see Dosage and Administration (2.7)].

Serious Psychiatric and Behavioral Reactions

Counsel patients, families, and caregivers of patients of the need to monitor for the emergence of anger, aggression, hostility, hallucinations, delusions, confusion, unusual changes in mood, personality, or behavior, and other behavioral symptoms. Advise them to report any such symptoms immediately to their healthcare providers [see Warnings and Precautions (5.1)].

Suicidal Thinking and Behavior

Counsel patients, their caregivers, and families that AEDs, including FYCOMPA, may increase the risk of suicidal thinking and behavior and advise them of the need to be alert for the emergence or worsening of symptoms of depression, any unusual changes in mood or behavior, or the emergence of suicidal thoughts, behavior, or thoughts about self-harm. Instruct patients, caregivers, and families to report behaviors of concern immediately to healthcare providers [see Warnings and Precautions (5.2)].

Neurologic Effects: Dizziness, Gait Disturbance, Somnolence, and Fatigue

Counsel patients that FYCOMPA may cause dizziness, gait disturbance, somnolence, and fatigue. Advise patients taking FYCOMPA not to drive, operate complex machinery, or engage in other hazardous activities until they have become accustomed to any such effects associated with FYCOMPA [see Warnings and Precautions (5.3)].

Falls

Counsel patients that FYCOMPA may cause falls and injuries [see Warnings and Precautions (5.4)].

DRESS/Multi-organ Hypersensitivity

Instruct patients that a fever associated with signs of other organ system involvement (e.g., rash, lymphadenopathy, hepatic dysfunction) may be drug-related and should be reported to their healthcare provider immediately [see Warnings and Precautions (5.5)].

Withdrawal of Antiepileptic Drugs

Counsel patients that abrupt discontinuation of FYCOMPA may increase seizure frequency [see Warnings and Precautions (5.6)].

Contraceptives

Counsel females of reproductive potential that FYCOMPA may decrease efficacy of contraceptives containing levonorgestrel, and advise them to use an additional non-hormonal form of contraception while using FYCOMPA and for a month after discontinuation [see Drug Interactions (7.1), Use in Specific Populations (8.3)].

Alcohol and Other CNS Depressants

Counsel patients that FYCOMPA may enhance the impairment effects of alcohol. These effects may also be seen if FYCOMPA is taken with other CNS depressants [see Drug Interactions (7.3)].

Missed Doses

Counsel patients that if they miss a dose, they should resume dosing the following day at their prescribed daily dose. Instruct patients to contact their physician if more than one day of dosing is missed.

Controlled Substance

Counsel patients that FYCOMPA is a controlled substance that can be misused and abused [see Drug Abuse and Dependence (9.1)].

Pregnancy Registry

Advise women who are exposed to FYCOMPA during pregnancy that there is a pregnancy exposure registry that monitors pregnancy outcomes. Encourage these patients to enroll in the NAAED Pregnancy Registry [see Use in Specific Populations (8.1)].

FYCOMPA® is a registered trademark owned by Catalyst Pharmaceuticals, Inc.

Manufactured by Eisai Inc. for Catalyst Pharmaceuticals, Inc.

Marketed by Catalyst Pharmaceuticals, Inc., Coral Gables, FL 33134

©2023 Catalyst Pharmaceuticals, Inc.

MEDICATION GUIDE

FYCOMPA® (fī-COM-puh) FYCOMPA® (fī-COM-puh)

(perampanel) (perampanel)

tablets, for oral use, CIII oral suspension, CIII

What is the most important information I should know about FYCOMPA?

1. FYCOMPA may cause mental (psychiatric) problems, including:
● new or worse aggressive behavior (including homicidal behavior), hostility, anger, anxiety, or irritability
● being suspicious or distrustful (believing things that are not true)
● seeing objects or hearing things that are not there
● confusion
● difficulty with memory
● other unusual or extreme changes in behavior or mood

Tell your healthcare provider right away if you have any new or worsening mental problems while taking FYCOMPA.

2. Like other antiepileptic drugs, FYCOMPA may cause suicidal thoughts or actions in a very small number of

people, about 1 in 500.

Call a healthcare provider right away if you have any of these symptoms, especially if they are new, worse,

or worry you:

● thoughts about suicide or dying ● attempt to commit suicide

● new or worse depression ● new or worse anxiety

● feeling agitated or restless ● panic attacks

● trouble sleeping (insomnia) ● new or worse irritability

● acting aggressive, being angry, or violent ● acting on dangerous impulses

● an extreme increase in activity and talking (mania) ● other unusual changes in behavior or mood

Suicidal thoughts or actions can be caused by things other than medicines. If you have suicidal thoughts or actions, your

healthcare provider may check for other causes.

How can I watch for early symptoms of suicidal thoughts and actions?

● Pay attention to any changes, especially sudden changes, in mood, behaviors, thoughts, or feelings.
● Keep all follow-up visits with your healthcare provider as scheduled.

Call your healthcare provider between visits as needed, especially if you are worried about symptoms.

Do not stop FYCOMPA without first talking with a healthcare provider. Stopping FYCOMPA suddenly can cause

serious problems. Stopping FYCOMPA suddenly can cause you to have seizures more often.

What is FYCOMPA?

FYCOMPA is a prescription medicine used:

● to treat partial-onset seizures with or without secondarily generalized seizures in people with epilepsy who are 4

years of age and older
● with other medicines to treat primary generalized tonic-clonic seizures in people with epilepsy who are 12 years of

age and older

FYCOMPA is a controlled substance (CIII) because it can be abused or lead to drug dependence. Keep your FYCOMPA

in a safe place to protect it from theft. Never give your FYCOMPA to anyone else because it may harm them. Selling or

giving away this medicine is against the law.

It is not known if FYCOMPA is safe and effective for partial onset seizures in children under 4 years of age or for

primary generalized tonic clonic seizures in patients under 12 years of age.

Before taking FYCOMPA, tell your healthcare provider about all of your medical conditions, including if you:

● have or have had depression, mood problems, aggressive or hostile behavior (for example, homicidal behavior),

suicidal thoughts or behavior, or other psychiatric problems.
● have liver or kidney problems
● drink alcohol
● have abused prescription medicines, street drugs, or alcohol in the past
● are pregnant or plan to become pregnant. It is not known if FYCOMPA will harm your unborn baby.
○ If you become pregnant while taking FYCOMPA, talk to your healthcare provider about registering with the North

American Antiepileptic Drug Pregnancy Registry. You can enroll in this registry by calling 1-888-233-2334 or go

to http://www.aedpregnancyregistry.org. The purpose of this registry is to collect information about the safety of

FYCOMPA and other antiepileptic medicine during pregnancy.
● are breastfeeding or plan to breastfeed. It is not known if FYCOMPA passes into your breast milk. Talk to your

healthcare provider about the best way to feed your baby if you take FYCOMPA. You and your healthcare provider

should decide if you will take FYCOMPA or breastfeed. You should not do both.

Tell your healthcare provider about all the medicines you take, including prescription and over-the-counter

medicines, vitamins, and herbal supplements.

Taking FYCOMPA with certain other medicines can cause side effects or reduce the benefit of either drug. Especially

tell your healthcare provider if you take:

● contraceptives (birth control). FYCOMPA may lower your contraceptives ability to prevent pregnancy if your

contraceptive contains levonorgestrel. Use an additional non-hormonal form of contraception (like condoms or a

diaphragm and spermicide) while using FYCOMPA and for 1 month after you have stopped taking FYCOMPA.
● carbamazepine (CARBATROL, TEGRETOL, TEGRETOL-XR, EQUETRO, EPITOL)
● phenytoin (DILANTIN, PHENYTEK)
● oxcarbazepine (TRILEPTAL)
● rifampin (RIFADIN, RIMACTANE)
● St. Johns Wort

How should I take FYCOMPA?

● See the Instructions for Use below for complete information on how to use the dosing syringes and how to measure

the dose of FYCOMPA Oral Suspension.
● Take FYCOMPA exactly as your healthcare provider tells you. Your healthcare provider will tell you how much

FYCOMPA to take and when to take it. FYCOMPA is usually taken 1 time a day at bedtime.
● Your healthcare provider may change the dose. Do not change the dose without talking to your healthcare provider.
● If you take FYCOMPA Oral Suspension, shake the bottle well before you take each dose.
● Measure the dose of FYCOMPA Oral Suspension using the bottle adapter and dosing syringes provided. Do not use

a household teaspoon.
● Talk to your healthcare provider about what to do if you miss more than 1 dose of FYCOMPA.
● If you take too much FYCOMPA, call your local Poison Control Center or go to the nearest hospital emergency room right away.

What should I avoid while taking FYCOMPA?

● Do not drive, operate heavy machinery, or do other dangerous activities until you know how FYCOMPA affects you.

FYCOMPA may make you dizzy, sleepy, or tired.

● Do not drink alcohol or take other medicines that make you sleepy or dizzy while taking FYCOMPA until you talk to

your healthcare provider. FYCOMPA taken with alcohol or medicines that cause sleepiness or dizziness may make

your sleepiness or dizziness worse. FYCOMPA when taken with alcohol may also make your mood worse, increase

anger, confusion, and depression.

What are the possible side effects of FYCOMPA?

See What is the most important information I should know about FYCOMPA?

FYCOMPA may cause other serious side effects, including:

● Dizziness, vertigo (sense of spinning), and problems walking normally. You may have problems walking

normally if you are unsteady because you feel dizzy. These symptoms can increase when the dose of FYCOMPA is

increased. Your risk of feeling dizzy and having problems walking normally may be higher if you are elderly.
● Sleepiness and tiredness. See What should I avoid while taking FYCOMPA?
● Increased risk of falls. Taking FYCOMPA can increase your chance of falling. These falls can cause serious injuries.

Your risk of falling may be higher if you are elderly.
● A serious allergic reaction that may affect your skin or other parts of your body such as your liver, kidneys,

heart, or blood cells. This allergic reaction can be life-threatening and can cause death. Call your healthcare

provider right away if you have:
○ a skin rash, hives
○ fever or swollen glands that do not go away
○ swelling of your face
○ shortness of breath, swelling of the legs, yellowing of the skin or whites of the eyes, or dark urine.

The most common side effects of FYCOMPA include:

● dizziness ● nausea and vomiting ● headache

● sleepiness ● weight gain ● bruising

● tiredness ● vertigo (sense of spinning) ● abdominal pain

● irritability ● problems walking normally ● anxiety

● falls ● problems with muscle coordination

These are not all of the possible side effects of FYCOMPA. For more information ask your healthcare provider or

pharmacist.

Call your doctor for medical advice about side effects. You may report side effects to FDA at 1-800-FDA-1088.

How should I store FYCOMPA?

● Store FYCOMPA tablets at room temperature between 68°F to 77°F (20°C to 25°C).
● Store FYCOMPA oral suspension below 86°F (30°C). Do not freeze.
● Replace the cap tightly after opening.
● Use FYCOMPA oral suspension within 90 days after the bottle is first opened.

Keep FYCOMPA and all medicines out of the reach of children.

General information about the safe and effective use of FYCOMPA.

Medicines are sometimes prescribed for purposes other than those listed in a Medication Guide. Do not use FYCOMPA

for a condition for which it was not prescribed. Do not give FYCOMPA to other people, even if they have the same

symptoms you have. It may harm them. You can ask your pharmacist or healthcare provider for information about

FYCOMPA that is written for health professionals.

What are the ingredients in FYCOMPA?

Active ingredient: perampanel

Inactive ingredients (tablets): lactose monohydrate, low substituted hydroxypropyl cellulose, povidone, microcrystalline

cellulose, magnesium stearate, hypromellose, polyethylene glycol, talc, and titanium dioxide. Tablets of different

strengths also may contain yellow ferric oxide (10 mg and 2 mg), red ferric oxide (2 mg, 4 mg, 6 mg, 8 mg), black ferric

oxide (8 mg), and FD&C blue # 2 (indigo carmine) aluminum lake (10 mg and 12 mg).

Inactive ingredients (oral suspension): sorbitol, microcrystalline cellulose, carboxymethylcellulose sodium, poloxamer,

simethicone, citric acid, sodium benzoate, and purified water.

Marketed by Catalyst Pharmaceuticals, Inc., Coral Gables, FL 33134

Manufactured by Eisai Inc. for Catalyst Pharmaceuticals, Inc.

FYCOMPA® is a trademark owned by Catalyst Pharmaceuticals, Inc. For more information, go to www.FYCOMPA.com

or 1-844-347-3277.

©2023 Catalyst Pharmaceuticals, Inc.

This Medication Guide has been approved by the U.S. Food and Drug Administration Revised: 06/2023

Instructions for Use

FYCOMPA® (fī-COM-puh)

(perampanel)

Oral Suspension

Read this Instructions for Use before you start using FYCOMPA Oral Suspension and each time you get a refill. There

may be new information. This leaflet does not take the place of talking to your healthcare provider about your medical

condition or treatment.

Prepare the FYCOMPA Oral Suspension dose

You will need the following supplies: See Figure A

• FYCOMPA Oral Suspension bottle

• Bottle adapter

• Dosing syringe (2 dosing syringes are included in the FYCOMPA Oral Suspension box)

Figure A

Step 1. Remove the FYCOMPA Oral Suspension bottle, bottle adapter, and 2 syringes from the box. See Figure A

Step 2. Shake the bottle well before each use. See Figure B

Figure B

Step 3. Uncap the bottle and insert the bottle adapter into the bottle by pressing downward. See Figure C and Figure D

Figure C

Figure D

After the bottle adapter is in place, it cannot be removed.

Step 4. Check the dose in milliliters (mL) as prescribed by your healthcare provider. Find this number on the syringe. See Figure E

Figure E

Step 5. Push the plunger of the syringe all the way down then insert the syringe into the upright bottle through the

opening in the bottle adapter. See Figure F

Figure F

Step 6. With the syringe in place, turn the bottle upside down. Pull the plunger to withdraw the dose prescribed by your

healthcare provider (the amount of liquid medicine in Step 4). If you see air bubbles in the oral syringe, fully push in the

plunger so that the oral solution flows back into the bottle. Then, withdraw the prescribed dose of oral suspension. See Figure G

Figure G

Measure the mLs of medicine from the end of the plunger.

Step 7. If the dose is more than 20 mL, you can use:

• 2 syringes

or

• 1 syringe, taking 2 steps to draw up the medicine in that same syringe

For example:

If the dose is 24 mL, draw up 20 mL in the first syringe and the remaining 4 mL in the second syringe.

or

If the dose is 24 mL, draw up 20 mL in the single syringe and squirt the medicine into the mouth, then draw up the

remaining 4 mL in that same syringe.

If the dose is more than 20 mL, repeat Steps 4 through 6 when drawing up the remaining dose of medicine.

Step 8. Turn the bottle right-side up and remove the syringe from the bottle adapter. See Figure H

Figure H

Step 9. Slowly squirt the FYCOMPA oral suspension directly into the corner of the mouth until all of the liquid medicine is

given. If you need 2 syringes for the dose, slowly squirt the medicine from the first syringe into the mouth, then slowly

squirt the medicine from the second syringe into the mouth. See Figure I

Figure I

Step 10. Rinse the syringe (or syringes) with tap water after each use. See Figure J

• Fill a cup with water

• Pull back on the plunger and draw the water from the cup into the syringe

• Push down on the plunger to release the water into the sink

Figure J

Step 11. Cap the bottle tightly. The cap will fit over the bottle adapter. See Figure K

Figure K

How should I store FYCOMPA Oral Suspension?

- Store FYCOMPA oral suspension below 86°F (30°C). Do not freeze.
- Replace the cap tightly after opening.
- Use FYCOMPA oral suspension within 90 days after the bottle is first opened.
- After 90 days safely throw away any FYCOMPA Oral Suspension that has not been used.

This Instructions for Use has been approved by the U.S. Food and Drug Administration.

FYCOMPA® is a registered trademark owned by Catalyst Pharmaceuticals, Inc.

Marketed by Catalyst Pharmaceuticals, Inc., Coral Gables, FL 33134

©2023 Catalyst Pharmaceuticals, Inc.

Revised: 06/2023

PACKAGE LABEL

PRINCIPAL DISPLAY PANEL - 2 mg Tablet

NDC 69616-272-30

30 tablets

Rx only

Fycompa™(perampanel)tablets

CIII

2 mg

ATTENTION PHARMACIST:Dispense the accompanyingMedication Guide to each patient.

PACKAGE LABEL

PRINCIPAL DISPLAY PANEL - 2 mg Tablet

NDC 69616-272-14

14 tablets

Rx only

Fycompa(perampanel) tablets

CIII

2 mg

2 week sample Kit

PACKAGE LABEL

PRINCIPAL DISPLAY PANEL - 4 mg Tablet

NDC 69616-274-30

30 tablets

Rx only

Fycompa™(perampanel)tablets

CIII

4 mg

ATTENTION PHARMACIST: Dispense the accompanying Medication Guide to each patient.

PACKAGE LABEL

PRINCIPAL DISPLAY PANEL - 6 mg Tablet

NDC 69616-276-30

30 tablets

Rx only

Fycompa™(perampanel)tablets

CIII

6 mg

ATTENTION PHARMACIST: Dispense the accompanying Medication Guide to each patient.

PACKAGE LABEL

PRINCIPAL DISPLAY PANEL - 8 mg Tablet

NDC 69616-278-30

30 tablets

Rx only

Fycompa™(perampanel)tablets

CIII

8 mg

ATTENTION PHARMACIST: Dispense the accompanying Medication Guide to each patient.

PACKAGE LABEL

PRINCIPAL DISPLAY PANEL - 10 mg Tablet

NDC 69616-280-30

30 tablets

Rx only

Fycompa™(perampanel)tablets

CIII

10 mg

ATTENTION PHARMACIST: Dispense the accompanying Medication Guide to each patient.

PACKAGE LABEL

PRINCIPAL DISPLAY PANEL - 12 mg Tablet

NDC 69616-282-30

30 tablets

Rx only

Fycompa™(perampanel)tablets

CIII

12 mg

ATTENTION PHARMACIST: Dispense the accompanying Medication Guide to each patient.

PACKAGE LABEL

PRINCIPAL DISPLAY PANEL - 0.5 mg/mL Oral Suspension

NDC 69616-290-38

0.5 mg/mL

Rx only

Fycompa® (perampanel)ORAL SUSPENSION

CIII

340 mL